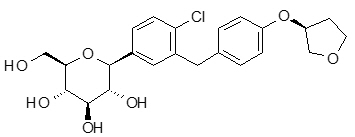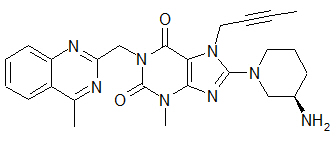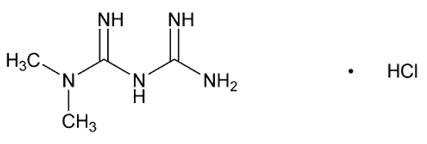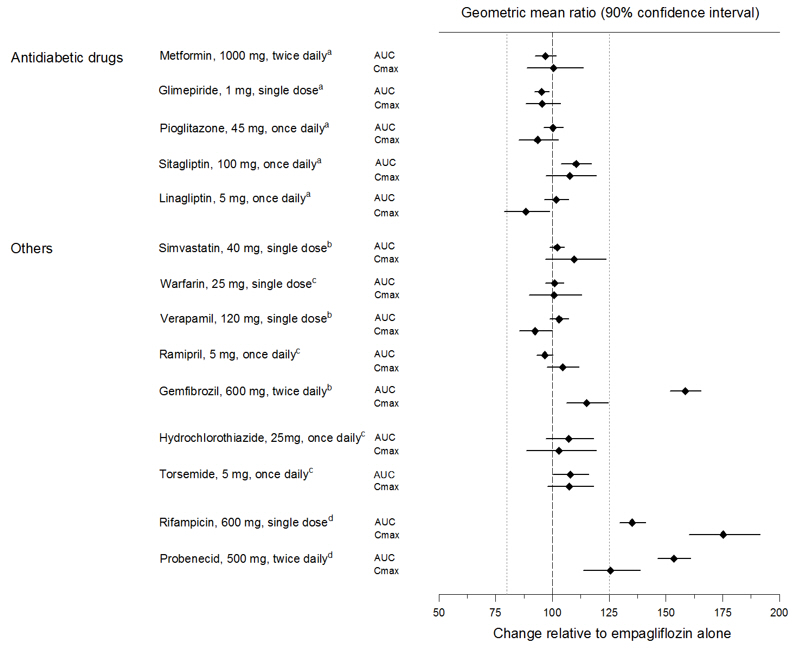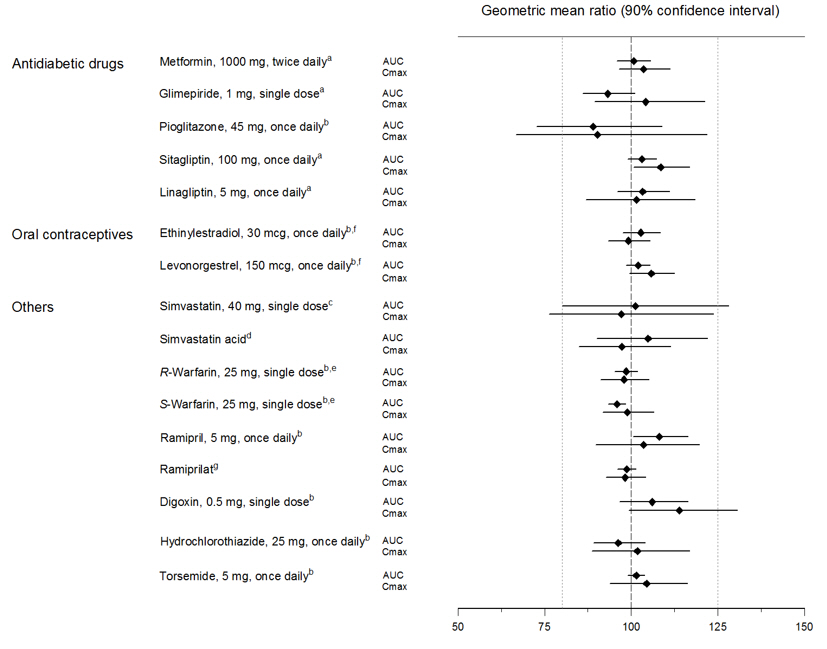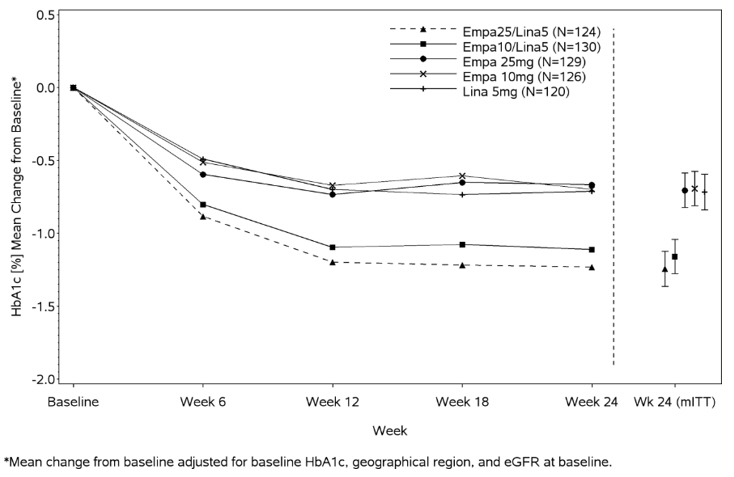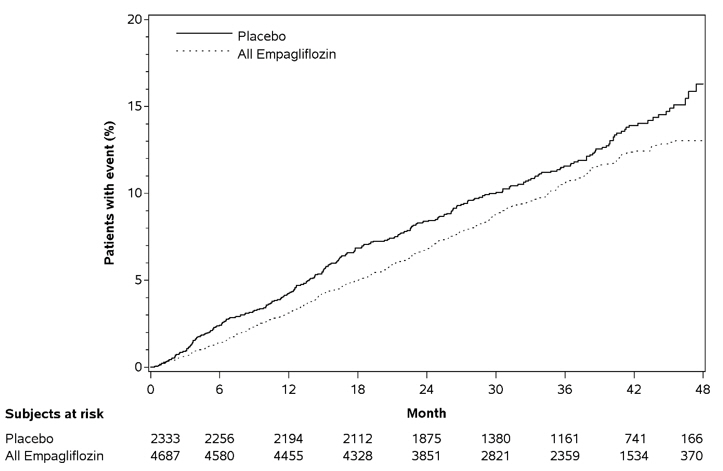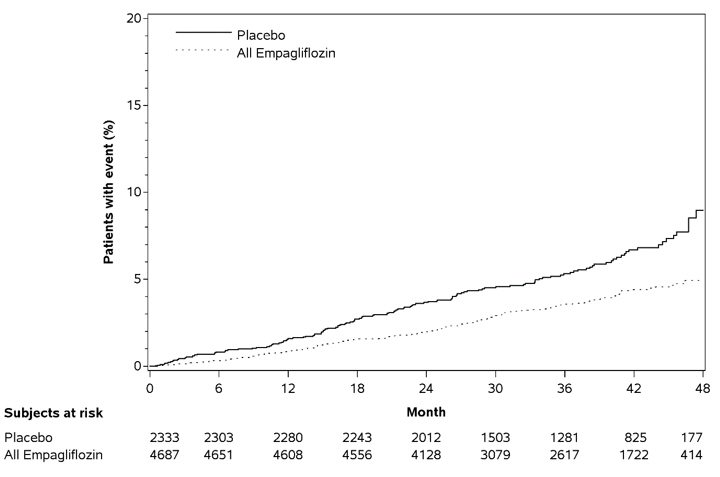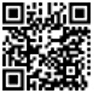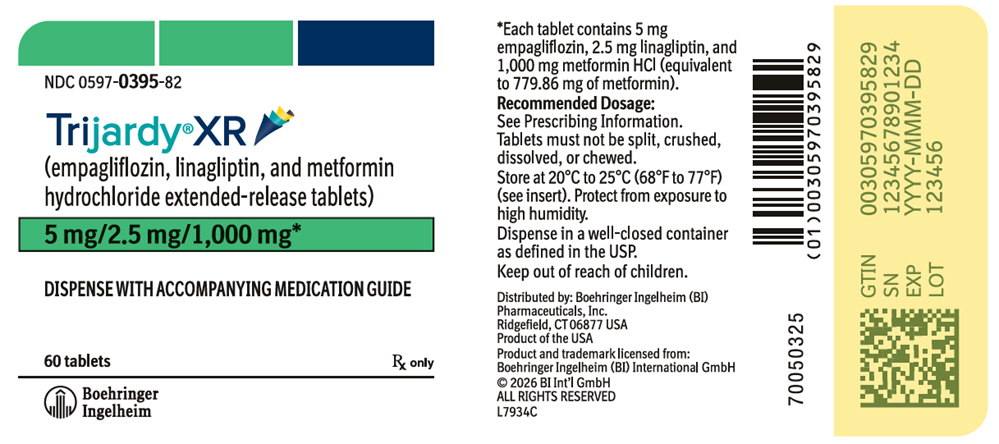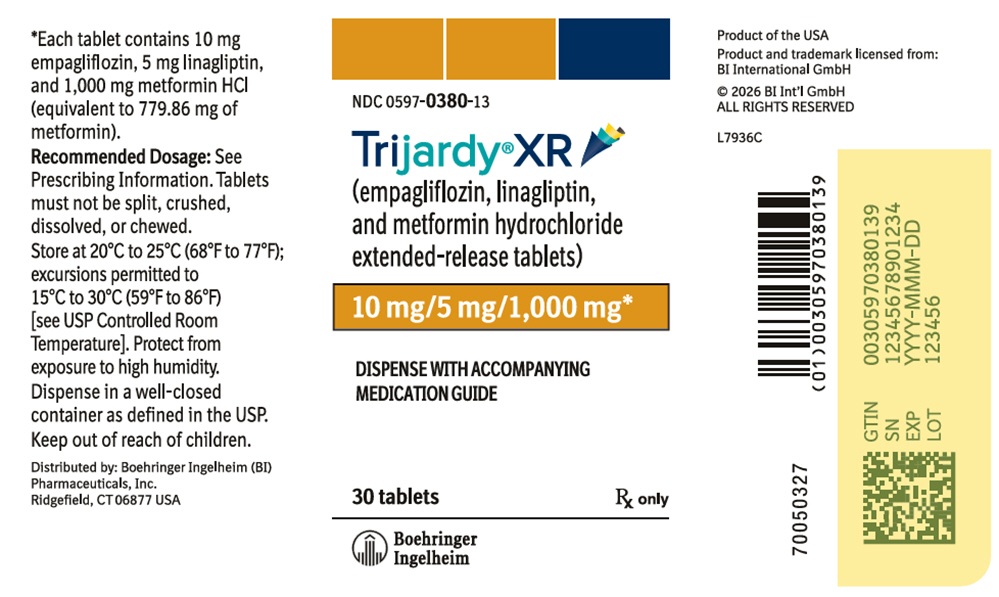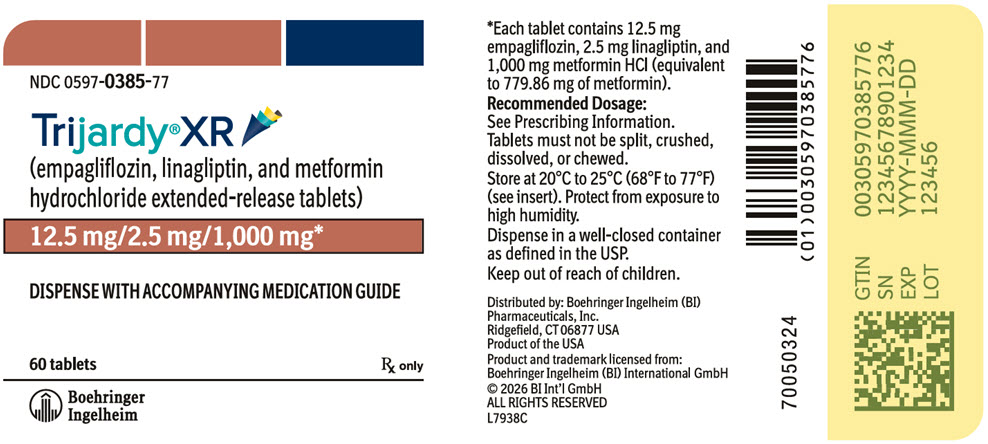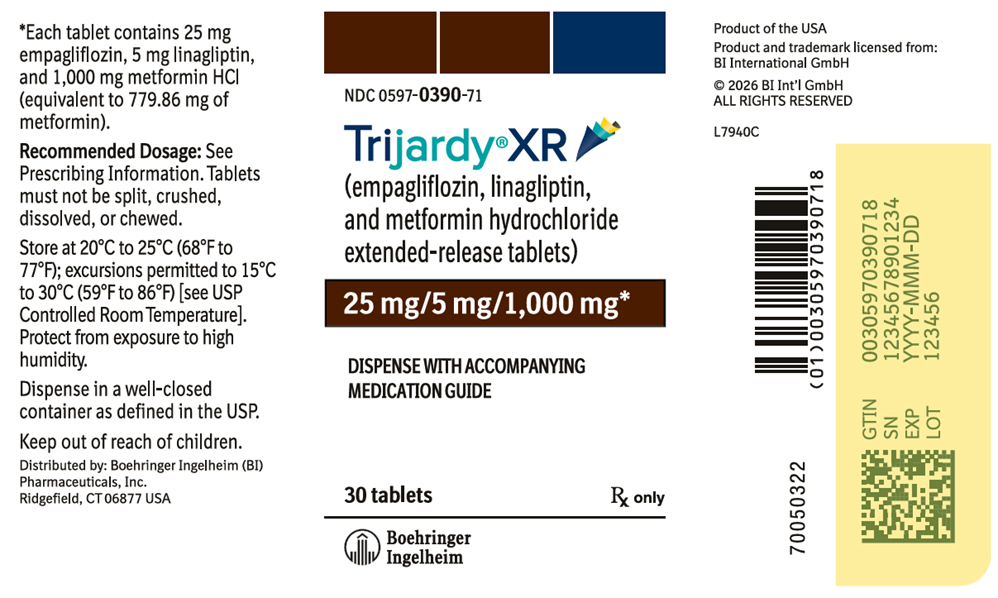 DRUG LABEL: Trijardy XR
NDC: 0597-0395 | Form: TABLET, EXTENDED RELEASE
Manufacturer: Boehringer Ingelheim Pharmaceuticals, Inc.
Category: prescription | Type: HUMAN PRESCRIPTION DRUG LABEL
Date: 20260130

ACTIVE INGREDIENTS: EMPAGLIFLOZIN 5 mg/1 1; LINAGLIPTIN 2.5 mg/1 1; METFORMIN HYDROCHLORIDE 1000 mg/1 1

HIGHLIGHTS OF PRESCRIBING INFORMATION

These highlights do not include all the information needed to use TRIJARDY XR safely and effectively. See full prescribing information for TRIJARDY XR.
TRIJARDY® XR (empagliflozin, linagliptin, and metformin hydrochloride extended-release tablets), for oral use
Initial U.S. Approval: 2020

WARNING: LACTIC ACIDOSIS

See full prescribing information for complete boxed warning.

- Postmarketing cases of metformin-associated lactic acidosis have resulted in death, hypothermia, hypotension, and resistant bradyarrhythmias. Symptoms included malaise, myalgias, respiratory distress, somnolence, and abdominal pain. Laboratory abnormalities included elevated blood lactate levels, anion gap acidosis, increased lactate/pyruvate ratio; and metformin plasma levels generally >5 mcg/mL. (5.1)
- Risk factors include renal impairment, concomitant use of certain drugs, age ≥65 years old, radiological studies with contrast, surgery and other procedures, hypoxic states, excessive alcohol intake, and hepatic impairment. Steps to reduce the risk of and manage metformin-associated lactic acidosis in these high risk groups are provided in the Full Prescribing Information. (5.1)
- If lactic acidosis is suspected, discontinue TRIJARDY XR and institute general supportive measures in a hospital setting. Prompt hemodialysis is recommended. (5.1)

RECENT MAJOR CHANGES

Warnings and Precautions (5.5) | 10/2025

1 INDICATIONS AND USAGE

TRIJARDY XR is a combination of empagliflozin, a sodium-glucose co-transporter 2 (SGLT2) inhibitor, linagliptin, a dipeptidyl peptidase-4 (DPP-4) inhibitor, and metformin hydrochloride (HCl), a biguanide, indicated as an adjunct to diet and exercise to improve glycemic control in adults with type 2 diabetes mellitus.

Empagliflozin is indicated to reduce the risk of cardiovascular (CV) death in adults with type 2 diabetes mellitus and established CV disease. (1)

Limitations of Use

- Not recommended for use to improve glycemic control in patients with type 1 diabetes mellitus. It may increase the risk of diabetic ketoacidosis in these patients. (1)
- Has not been studied in patients with a history of pancreatitis. (1)

2 DOSAGE AND ADMINISTRATION

- Assess renal function before initiating and as clinically indicated. Assess volume status and correct volume depletion before initiating. (2.1)
- Individualize the starting dosage based on the patient's current regimen and renal function. (2.2, 2.3)
- Initiation is not recommended in patients with an eGFR less than 45 mL/min/1.73 m^2, due to the metformin HCl component. (2.3)
- The maximum recommended dosage of TRIJARDY XR is 25 mg empagliflozin, 5 mg linagliptin and 2,000 mg metformin HCl. (2.2)
- Take once daily with a meal in the morning. (2.2)
- Swallow whole; do not split, crush, dissolve, or chew. (2.2)
- TRIJARDY XR may need to be discontinued at time of, or prior to, iodinated contrast imaging procedures. (2.4)
- Withhold TRIJARDY XR for at least 3 days, if possible, prior to surgery or procedures associated with prolonged fasting. (2.5)

3 DOSAGE FORMS AND STRENGTHS

Tablets:

- 5 mg empagliflozin/2.5 mg linagliptin/1,000 mg metformin HCl extended-release (3)
- 10 mg empagliflozin/5 mg linagliptin/1,000 mg metformin HCl extended-release (3)
- 12.5 mg empagliflozin/2.5 mg linagliptin/1,000 mg metformin HCl extended-release (3)
- 25 mg empagliflozin/5 mg linagliptin/1,000 mg metformin HCl extended-release (3)

4 CONTRAINDICATIONS

- Severe renal impairment (eGFR below 30 mL/min/1.73 m^2). (4)
- Metabolic acidosis, including diabetic ketoacidosis. (4)
- Hypersensitivity to empagliflozin, linagliptin, metformin HCl, or any of the excipients in TRIJARDY XR. (4)

5 WARNINGS AND PRECAUTIONS

- Diabetic Ketoacidosis in Patients with Type 1 Diabetes Mellitus and Other Ketoacidosis: Consider ketone monitoring in patients at risk of ketoacidosis, as indicated. Assess for ketoacidosis regardless of presenting blood glucose levels and discontinue TRIJARDY XR if ketoacidosis is suspected. Monitor patients for resolution of ketoacidosis before restarting. (5.2)
- Pancreatitis: There have been reports of acute pancreatitis, including fatal pancreatitis. If pancreatitis is suspected, promptly discontinue TRIJARDY XR. (5.3)
- Volume Depletion: Before initiating TRIJARDY XR, assess volume status and renal function in patients with impaired renal function, elderly patients, or patients on loop diuretics. Monitor for signs and symptoms during therapy. (5.4)
- Genitourinary Infections, including Urosepsis, Pyelonephritis, Necrotizing Fasciitis of the Perineum (Fournier's Gangrene), and Genital Mycotic Infections: Monitor patients for signs and symptoms of genitourinary infections and treat promptly, if indicated. Immediately evaluate patients presenting with pain or tenderness, erythema, or swelling in the genital or perineal area, along with fever or malaise, for necrotizing fasciitis and if suspected, discontinue TRIJARDY XR, and promptly institute appropriate medical and/or surgical intervention. (5.5)
- Hypoglycemia: Consider lowering the dosage of insulin secretagogue or insulin to reduce the risk of hypoglycemia when initiating TRIJARDY XR. (5.6)
- Lower Limb Amputation: Monitor patients for infections or ulcers of lower limbs, and institute appropriate treatment. (5.7)
- Hypersensitivity Reactions: Serious hypersensitivity reactions (e.g., anaphylaxis, angioedema, and exfoliative skin conditions) have occurred with empagliflozin and linagliptin. If hypersensitivity reactions occur, discontinue TRIJARDY XR, treat promptly, and monitor until signs and symptoms resolve. (5.8)
- Vitamin B12 Deficiency: Metformin may lower vitamin B12 levels. Measure hematologic parameters annually and vitamin B12 at 2 to 3 year intervals and manage any abnormalities. (5.9)
- Arthralgia: Severe and disabling arthralgia has been reported in patients taking linagliptin. Consider as a possible cause for severe joint pain and discontinue TRIJARDY XR if appropriate. (5.10)
- Bullous Pemphigoid: There have been reports of bullous pemphigoid requiring hospitalization. Tell patients to report development of blisters or erosions. If bullous pemphigoid is suspected, discontinue TRIJARDY XR. (5.11)
- Heart Failure: Heart failure has been observed with two other members of the DPP-4 inhibitor class. Consider risks and benefits of TRIJARDY XR in patients who have known risk factors for heart failure. Monitor for signs and symptoms. (5.12)

6 ADVERSE REACTIONS

Most common adverse reactions (5% or greater incidence) were upper respiratory tract infection, urinary tract infection, nasopharyngitis, diarrhea, constipation, headache, and gastroenteritis. (6.1)

To report SUSPECTED ADVERSE REACTIONS, contact Boehringer Ingelheim Pharmaceuticals, Inc. at 1-800-542-6257, or FDA at 1-800-FDA-1088 or www.fda.gov/medwatch.

7 DRUG INTERACTIONS

- Carbonic Anhydrase Inhibitors: May increase risk of lactic acidosis. Consider more frequent monitoring. (7)
- Drugs that Reduce Metformin Clearance: May increase risk of lactic acidosis. Consider benefits and risks of concomitant use. (7)
- See full prescribing information for additional drug interactions and information on interference of TRIJARDY XR with laboratory tests. (7)

8 USE IN SPECIFIC POPULATIONS

- Pregnancy: Advise females of the potential risk to a fetus especially during the second and third trimesters. (8.1)
- Lactation: Not recommended when breastfeeding. (8.2)
- Females and Males of Reproductive Potential: Advise premenopausal females of the potential for an unintended pregnancy. (8.3)
- Geriatric Patients: Higher incidence of adverse reactions related to volume depletion and reduced renal function. (8.5)
- Renal Impairment: Higher incidence of adverse reactions related to reduced renal function. (8.6)
- Hepatic Impairment: Avoid use in patients with hepatic impairment. (8.7)

FULL PRESCRIBING INFORMATION

WARNING: LACTIC ACIDOSIS

Postmarketing cases of metformin-associated lactic acidosis have resulted in death, hypothermia, hypotension, and resistant bradyarrhythmias. The onset of metformin-associated lactic acidosis is often subtle, accompanied only by nonspecific symptoms such as malaise, myalgias, respiratory distress, somnolence, and abdominal pain. Metformin-associated lactic acidosis was characterized by elevated blood lactate levels (>5 mmol/Liter), anion gap acidosis (without evidence of ketonuria or ketonemia), an increased lactate/pyruvate ratio; and metformin plasma levels generally >5 mcg/mL [see Warnings and Precautions (5.1)].

Risk factors for metformin-associated lactic acidosis include renal impairment, concomitant use of certain drugs (e.g., carbonic anhydrase inhibitors such as topiramate), age 65 years old or greater, having a radiological study with contrast, surgery and other procedures, hypoxic states (e.g., acute congestive heart failure), excessive alcohol intake, and hepatic impairment.

Steps to reduce the risk of and manage metformin-associated lactic acidosis in these high risk groups are provided in the full prescribing information [see Dosage and Administration (2.3), Contraindications (4), Warnings and Precautions (5.1), Drug Interactions (7), and Use in Specific Populations (8.6, 8.7)].

If metformin-associated lactic acidosis is suspected, immediately discontinue TRIJARDY XR and institute general supportive measures in a hospital setting. Prompt hemodialysis is recommended [see Warnings and Precautions (5.1)].

1 INDICATIONS AND USAGE

TRIJARDY XR is a combination of empagliflozin, linagliptin, and metformin hydrochloride (HCl) indicated as an adjunct to diet and exercise to improve glycemic control in adults with type 2 diabetes mellitus.

Empagliflozin is indicated to reduce the risk of cardiovascular (CV) death in adults with type 2 diabetes mellitus and established CV disease [see Clinical Studies (14.2)].

Limitations of Use

TRIJARDY XR is not recommended for use to improve glycemic control in patients with type 1 diabetes mellitus. It may increase the risk of diabetic ketoacidosis in these patients [see Warnings and Precautions (5.2)].

TRIJARDY XR has not been studied in patients with a history of pancreatitis. It is unknown whether patients with a history of pancreatitis are at an increased risk for the development of pancreatitis while using TRIJARDY XR [see Warnings and Precautions (5.3)].

2 DOSAGE AND ADMINISTRATION

2.1 Testing Prior to Initiation of TRIJARDY XR

- Assess renal function before initiating TRIJARDY XR and as clinically indicated [see Warnings and Precautions (5.1, 5.4)].
- Assess volume status. In patients with volume depletion, correct this condition before initiating TRIJARDY XR [see Warnings and Precautions (5.4) and Use in Specific Populations (8.5, 8.6)].

2.2 Recommended Dosage and Administration

- Individualize the starting dosage of TRIJARDY XR based on the patient's current regimen:
  - In patients on metformin HCl, with or without linagliptin, switch to TRIJARDY XR containing a similar total daily dosage of metformin HCl and a total daily dosage of empagliflozin 10 mg and linagliptin 5 mg;
  - In patients on metformin HCl and any regimen containing empagliflozin, with or without linagliptin, switch to TRIJARDY XR containing a similar total daily dosage of metformin HCl, the same total daily dosage of empagliflozin and linagliptin 5 mg.
- Monitor effectiveness and tolerability, and adjust dosing as appropriate, not to exceed the maximum recommended daily dosage of empagliflozin 25 mg, linagliptin 5 mg and metformin HCl 2,000 mg.
- Take TRIJARDY XR orally, once daily with a meal in the morning.
  - Take TRIJARDY XR 10 mg/5 mg/1,000 mg or TRIJARDY XR 25 mg/5 mg/1,000 mg as a single tablet once daily.
  - Take TRIJARDY XR 5 mg/2.5 mg/1,000 mg or TRIJARDY XR 12.5 mg/2.5 mg/1,000 mg as two tablets together once daily.
- Swallow TRIJARDY XR tablets whole. Do not split, crush, dissolve, or chew.

2.3 Dosage Recommendations in Patients with Renal Impairment

- Initiation of TRIJARDY XR is not recommended in patients with an eGFR less than 45 mL/min/1.73 m^2, due to the metformin HCl component.
- TRIJARDY XR is contraindicated in patients with an eGFR less than 30 mL/min/1.73 m^2 [see Contraindications (4), Warnings and Precautions (5.1, 5.4), and Use in Specific Populations (8.6)].

2.4 Discontinuation for Iodinated Contrast Imaging Procedures

Discontinue TRIJARDY XR at the time of, or prior to, an iodinated contrast imaging procedure in patients with an eGFR less than 60 mL/min/1.73 m^2; in patients with a history of liver disease, alcoholism or heart failure; or in patients who will be administered intra-arterial iodinated contrast. Re-evaluate eGFR 48 hours after the imaging procedure; restart TRIJARDY XR if renal function is stable [see Warnings and Precautions (5.1)].

2.5 Temporary Interruption for Surgery

Withhold TRIJARDY XR for at least 3 days, if possible, prior to surgery or procedures associated with prolonged fasting. Resume TRIJARDY XR when the patient is clinically stable and has resumed oral intake [see Warnings and Precautions (5.2) and Clinical Pharmacology (12.2)].

2.6 Recommendations Regarding Missed Dose

- If a dose is missed, instruct patients to take the dose as soon as possible.
- Advise patients not to double up the next dose.

3 DOSAGE FORMS AND STRENGTHS

TRIJARDY XR Tablets:

Empagliflozin Strength | Linagliptin Strength | Metformin HCl Extended-Release Strength | Color/Shape | Tablet Markings
5 mg | 2.5 mg | 1,000 mg | grey, oval-shaped, film-coated tablet | Printed on one side in white ink with the Boehringer Ingelheim company symbol and "395" on the top line and "5/2.5" on the bottom line.
10 mg | 5 mg | 1,000 mg | tan, oval-shaped, film-coated tablet | Printed on one side in white ink with the Boehringer Ingelheim company symbol and "380" on the top line and "10/5" on the bottom line.
12.5 mg | 2.5 mg | 1,000 mg | red, oval-shaped, film-coated tablet | Printed on one side in white ink with the Boehringer Ingelheim company symbol and "385" on the top line and "12.5/2.5" on the bottom line.
25 mg | 5 mg | 1,000 mg | brown, oval-shaped, film-coated tablet | Printed on one side in white ink with the Boehringer Ingelheim company symbol and "390" on the top line and "25/5" on the bottom line.

4 CONTRAINDICATIONS

TRIJARDY XR is contraindicated in patients with:

- severe renal impairment (eGFR less than 30 mL/min/1.73 m^2) [see Warnings and Precautions (5.1, 5.4) and Use in Specific Populations (8.6)].
- acute or chronic metabolic acidosis, including diabetic ketoacidosis [see Warnings and Precautions (5.1)].
- hypersensitivity to empagliflozin, linagliptin, metformin HCl or any of the excipients in TRIJARDY XR, reactions such as anaphylaxis, angioedema, exfoliative skin conditions, urticaria, or bronchial hyperreactivity have occurred [see Warnings and Precautions (5.8) and Adverse Reactions (6)].

5 WARNINGS AND PRECAUTIONS

5.1 Lactic Acidosis

There have been postmarketing cases of metformin-associated lactic acidosis, including fatal cases. These cases had a subtle onset and were accompanied by nonspecific symptoms such as malaise, myalgias, abdominal pain, respiratory distress, or increased somnolence; however, hypothermia, hypotension, and resistant bradyarrhythmias have occurred with severe acidosis. Metformin-associated lactic acidosis was characterized by elevated blood lactate concentrations (>5 mmol/Liter), anion gap acidosis (without evidence of ketonuria or ketonemia), and an increased lactate:pyruvate ratio; metformin plasma levels generally >5 mcg/mL. Metformin decreases liver uptake of lactate increasing lactate blood levels, which may increase the risk of lactic acidosis, especially in patients at risk.

If metformin-associated lactic acidosis is suspected, general supportive measures should be instituted promptly in a hospital setting, along with immediate discontinuation of TRIJARDY XR. In TRIJARDY XR-treated patients with a diagnosis or strong suspicion of lactic acidosis, prompt hemodialysis is recommended to correct the acidosis and remove accumulated metformin (metformin is dialyzable, with a clearance of up to 170 mL/minute under good hemodynamic conditions). Hemodialysis has often resulted in reversal of symptoms and recovery.

Educate patients and their families about the symptoms of lactic acidosis and if these symptoms occur instruct them to discontinue TRIJARDY XR and report these symptoms to their healthcare provider.

For each of the known and possible risk factors for metformin-associated lactic acidosis, recommendations to reduce the risk of and manage metformin-associated lactic acidosis are provided below:

Renal Impairment: The postmarketing metformin-associated lactic acidosis cases primarily occurred in patients with significant renal impairment. The risk of metformin accumulation and metformin-associated lactic acidosis increases with the severity of renal impairment because metformin is substantially excreted by the kidney. Clinical recommendations based upon the patient's renal function include [see Dosage and Administration (2.3) and Clinical Pharmacology (12.3)]:

- Before initiating TRIJARDY XR, obtain an estimated glomerular filtration rate (eGFR).
- TRIJARDY XR is contraindicated in patients with an eGFR below 30 mL/min/1.73 m^2 [see Contraindications (4)].
- Obtain an eGFR at least annually in all patients taking TRIJARDY XR. In patients at increased risk for the development of renal impairment (e.g., the elderly), renal function should be assessed more frequently.

Drug Interactions: The concomitant use of TRIJARDY XR with specific drugs may increase the risk of metformin-associated lactic acidosis: those that impair renal function, result in significant hemodynamic change, interfere with acid-base balance or increase metformin accumulation [see Drug Interactions (7)]. Therefore, consider more frequent monitoring of patients.

Age 65 or Greater: The risk of metformin-associated lactic acidosis increases with the patient's age because elderly patients have a greater likelihood of having hepatic, renal, or cardiac impairment than younger patients. Assess renal function more frequently in elderly patients [see Use in Specific Populations (8.5)].

Radiological Studies with Contrast: Administration of intravascular iodinated contrast agents in metformin-treated patients has led to an acute decrease in renal function and the occurrence of lactic acidosis. Stop TRIJARDY XR at the time of, or prior to, an iodinated contrast imaging procedure in patients with an eGFR less than 60 mL/min/1.73 m^2; in patients with a history of hepatic impairment, alcoholism, or heart failure; or in patients who will be administered intra-arterial iodinated contrast. Re-evaluate eGFR 48 hours after the imaging procedure, and restart TRIJARDY XR if renal function is stable.

Surgery and Other Procedures: Withholding of food and fluids during surgical or other procedures may increase the risk for volume depletion, hypotension and renal impairment. TRIJARDY XR should be temporarily discontinued while patients have restricted food and fluid intake.

Hypoxic States: Several of the postmarketing cases of metformin-associated lactic acidosis occurred in the setting of acute congestive heart failure (particularly when accompanied by hypoperfusion and hypoxemia). Cardiovascular collapse (shock), acute myocardial infarction, sepsis, and other conditions associated with hypoxemia have been associated with lactic acidosis and may also cause prerenal azotemia. When such events occur, discontinue TRIJARDY XR.

Excessive Alcohol Intake: Alcohol potentiates the effect of metformin on lactate metabolism and this may increase the risk of metformin-associated lactic acidosis. Warn patients against excessive alcohol intake while receiving TRIJARDY XR.

Hepatic Impairment: Patients with hepatic impairment have developed cases of metformin-associated lactic acidosis. This may be due to impaired lactate clearance resulting in higher lactate blood levels. Therefore, avoid use of TRIJARDY XR in patients with clinical or laboratory evidence of hepatic disease.

5.2 Diabetic Ketoacidosis in Patients with Type 1 Diabetes Mellitus and Other Ketoacidosis

In patients with type 1 diabetes mellitus, empagliflozin, a component of TRIJARDY XR, significantly increases the risk of diabetic ketoacidosis, a life-threatening event, beyond the background rate. In placebo-controlled trials of patients with type 1 diabetes mellitus, the risk of ketoacidosis was markedly increased in patients who received sodium glucose co-transporter 2 (SGLT2) inhibitors compared to patients who received placebo and fatal ketoacidosis has occurred with empagliflozin. TRIJARDY XR is not indicated for glycemic control in patients with type 1 diabetes mellitus.

Type 2 diabetes mellitus and pancreatic disorders (e.g., history of pancreatitis or pancreatic surgery) are also risk factors for ketoacidosis. There have been postmarketing reports of fatal events of ketoacidosis in patients with type 2 diabetes mellitus using SGLT2 inhibitors, including empagliflozin.

Precipitating conditions for diabetic ketoacidosis or other ketoacidosis include under-insulinization due to insulin dose reduction or missed insulin doses, acute febrile illness, reduced caloric intake, ketogenic diet, surgery, volume depletion, and alcohol abuse.

Signs and symptoms are consistent with dehydration and severe metabolic acidosis and include nausea, vomiting, abdominal pain, generalized malaise, and shortness of breath. Blood glucose levels at presentation may be below those typically expected for diabetic ketoacidosis (e.g., less than 250 mg/dL). Ketoacidosis and glucosuria may persist longer than typically expected. Urinary glucose excretion persists for 3 days after discontinuing TRIJARDY XR [see Clinical Pharmacology (12.2)]; however, there have been postmarketing reports of ketoacidosis and/or glucosuria lasting greater than 6 days and some up to 2 weeks after discontinuation of SGLT2 inhibitors.

Consider ketone monitoring in patients at risk for ketoacidosis if indicated by the clinical situation. Assess for ketoacidosis regardless of presenting blood glucose levels in patients who present with signs and symptoms consistent with severe metabolic acidosis. If ketoacidosis is suspected, discontinue TRIJARDY XR, promptly evaluate, and treat ketoacidosis, if confirmed. Monitor patients for resolution of ketoacidosis before restarting TRIJARDY XR.

Withhold TRIJARDY XR, if possible, in temporary clinical situations that could predispose patients to ketoacidosis. Resume TRIJARDY XR when the patient is clinically stable and has resumed oral intake [see Dosage and Administration (2.5)].

Educate all patients on the signs and symptoms of ketoacidosis and instruct patients to discontinue TRIJARDY XR and seek medical attention immediately if signs and symptoms occur.

5.3 Pancreatitis

Acute pancreatitis, including fatal pancreatitis, has been reported in patients treated with linagliptin. In the CARMELINA trial [see Clinical Studies (14.3)], acute pancreatitis was reported in 9 (0.3%) patients treated with linagliptin and in 5 (0.1%) patients treated with placebo. Two patients treated with linagliptin in the CARMELINA trial had acute pancreatitis with a fatal outcome. There have been postmarketing reports of acute pancreatitis, including fatal pancreatitis, in patients treated with linagliptin.

Take careful notice of potential signs and symptoms of pancreatitis. If pancreatitis is suspected, promptly discontinue TRIJARDY XR and initiate appropriate management. It is unknown whether patients with a history of pancreatitis are at increased risk for the development of pancreatitis while using TRIJARDY XR.

5.4 Volume Depletion

Empagliflozin can cause intravascular volume depletion which may sometimes manifest as symptomatic hypotension or acute transient changes in creatinine [see Adverse Reactions (6.1)]. There have been post-marketing reports of acute kidney injury, some requiring hospitalization and dialysis, in patients with type 2 diabetes mellitus receiving SGLT2 inhibitors, including empagliflozin. Patients with impaired renal function (eGFR less than 60 mL/min/1.73 m^2), elderly patients, or patients on loop diuretics may be at increased risk for volume depletion or hypotension. Before initiating TRIJARDY XR in patients with one or more of these characteristics, assess volume status and renal function. In patients with volume depletion, correct this condition before initiating TRIJARDY XR. Monitor for signs and symptoms of volume depletion, and renal function after initiating therapy.

5.5 Genitourinary Infections, including Urosepsis, Pyelonephritis, Necrotizing Fasciitis of the Perineum (Fournier's Gangrene), and Genital Mycotic Infections

Empagliflozin increases urinary glucose excretion [see Clinical Pharmacology (12.2)] and increases the risk of genitourinary infections including urinary tract infections and genital mycotic infections in both male and female patients [see Adverse Reactions (6.1)].

Serious genitourinary infections, including urosepsis, pyelonephritis, and necrotizing fasciitis of the perineum (Fournier's gangrene, a rare life-threatening infection requiring urgent surgical intervention), have occurred in patients with and without diabetes mellitus receiving SGLT2 inhibitors, including empagliflozin [see Adverse Reactions (6.2)]. Cases have required hospitalization. In patients with Fournier's gangrene, serious outcomes have included multiple surgeries and death. TRIJARDY XR is only indicated for use in patients with type 2 diabetes mellitus.

Patients with history of chronic or recurrent genitourinary infections are more likely to develop genitourinary infections when using TRIJARDY XR. Monitor patients for signs and symptoms of genitourinary infections and treat promptly, if indicated.

Immediately evaluate patients presenting with pain or tenderness, erythema, or swelling in the genital or perineal area, along with fever or malaise, for necrotizing fasciitis. If suspected, discontinue TRIJARDY XR and promptly institute appropriate medical and/or surgical intervention.

5.6 Hypoglycemia with Concomitant Use with Insulin and Insulin Secretagogues

Insulin and insulin secretagogues are known to cause hypoglycemia. The risk of hypoglycemia is increased when TRIJARDY XR is used in combination with an insulin secretagogue (e.g., sulfonylurea) or insulin. Therefore, a lower dosage of the insulin secretagogue or insulin may be required to reduce the risk of hypoglycemia when used in combination with TRIJARDY XR.

5.7 Lower Limb Amputation

In some clinical studies with SGLT2 inhibitors an imbalance in the incidence of lower limb amputation has been observed. Across four empagliflozin outcome trials, lower limb amputation event rates were 4.3 and 5.0 events per 1,000 patient-years in the placebo group and the empagliflozin 10 mg or 25 mg dose group, respectively, with a HR of 1.05 (95 % CI) (0.81, 1.36).

In a long-term cardio-renal outcome trial, in patients with chronic kidney disease, the occurrence of lower limb amputations was reported with event rates of 2.9, and 4.3 events per 1,000 patient-years in the placebo, and empagliflozin 10 mg treatment arms, respectively. Amputation of the toe and mid-foot were most frequent (21 out of 28 empagliflozin 10 mg treated patients with lower limb amputations), and some involving above and below the knee. Some patients had multiple amputations. TRIJARDY XR is not indicated for the treatment of chronic kidney disease.

Peripheral artery disease, and diabetic foot infection (including osteomyelitis), were the most common precipitating medical events leading to the need for an amputation. The risk of amputation was highest in patients with a baseline history of diabetic foot, peripheral artery disease (including previous amputation) or diabetes.

Counsel patients about the importance of routine preventative foot care. Monitor patients receiving TRIJARDY XR for signs and symptoms of diabetic foot infection (including osteomyelitis), new pain or tenderness, sores or ulcers involving the lower limbs, and institute appropriate treatment.

5.8 Hypersensitivity Reactions

There have been postmarketing reports of serious hypersensitivity reactions in patients treated with linagliptin. These reactions include anaphylaxis, angioedema, and exfoliative skin conditions. Onset of these reactions occurred predominantly within the first 3 months after initiation of treatment with linagliptin, with some reports occurring after the first dose.

Angioedema has also been reported with other dipeptidyl peptidase-4 (DPP-4) inhibitors. Use caution in a patient with a history of angioedema to another DPP-4 inhibitor because it is unknown whether such patients will be predisposed to angioedema with TRIJARDY XR.

There have been postmarketing reports of serious hypersensitivity reactions (e.g., angioedema) in patients treated with empagliflozin.

If a hypersensitivity reaction occurs, discontinue TRIJARDY XR, treat promptly per standard of care, and monitor until signs and symptoms resolve. TRIJARDY XR is contraindicated in patients with hypersensitivity to linagliptin, empagliflozin or any of the excipients in TRIJARDY XR [see Contraindications (4)].

5.9 Vitamin B12 Deficiency

In metformin HCl clinical trials of 29-week duration, a decrease to subnormal levels of previously normal serum vitamin B12 levels was observed in approximately 7% of metformin-treated patients. Such decrease, possibly due to interference with B12 absorption from the B12-intrinsic factor complex, may be associated with anemia but appears to be rapidly reversible with discontinuation of metformin or vitamin B12 supplementation. Certain individuals (those with inadequate vitamin B12 or calcium intake or absorption) appear to be predisposed to developing subnormal vitamin B12 levels. Measure hematologic parameters on an annual basis and vitamin B12 at 2 to 3 year intervals in patients on TRIJARDY XR and manage any abnormalities [see Adverse Reactions (6.1)].

5.10 Severe and Disabling Arthralgia

There have been postmarketing reports of severe and disabling arthralgia in patients taking linagliptin. The time to onset of symptoms following initiation of drug therapy varied from one day to years. Patients experienced relief of symptoms upon discontinuation of the medication. A subset of patients experienced a recurrence of symptoms when restarting the same drug or a different DPP-4 inhibitor. Consider DPP-4 inhibitors as a possible cause for severe joint pain and discontinue drug if appropriate.

5.11 Bullous Pemphigoid

Bullous pemphigoid was reported in 7 (0.2%) patients treated with linagliptin compared to none in patients treated with placebo in the CARMELINA trial [see Clinical Studies (14.3)], and 3 of these patients were hospitalized due to bullous pemphigoid. Postmarketing cases of bullous pemphigoid requiring hospitalization have been reported with DPP-4 inhibitor use. In reported cases, patients typically recovered with topical or systemic immunosuppressive treatment and discontinuation of the DPP-4 inhibitor. Tell patients to report development of blisters or erosions while receiving TRIJARDY XR. If bullous pemphigoid is suspected, TRIJARDY XR should be discontinued and referral to a dermatologist should be considered for diagnosis and appropriate treatment.

5.12 Heart Failure

An association between DPP-4 inhibitor treatment and heart failure has been observed in cardiovascular outcomes trials for two other members of the DPP-4 inhibitor class. These trials evaluated patients with type 2 diabetes mellitus and atherosclerotic cardiovascular disease.

Consider the risks and benefits of TRIJARDY XR prior to initiating treatment in patients at risk for heart failure, such as those with a prior history of heart failure and a history of renal impairment, and observe these patients for signs and symptoms of heart failure during therapy. Advise patients of the characteristic symptoms of heart failure and to immediately report such symptoms. If heart failure develops, evaluate and manage according to current standards of care and consider discontinuation of TRIJARDY XR.

6 ADVERSE REACTIONS

The following important adverse reactions are described below and elsewhere in the labeling:

- Lactic Acidosis [see Boxed Warning and Warnings and Precautions (5.1)]
- Diabetic Ketoacidosis in Patients with Type 1 Diabetes Mellitus and Other Ketoacidosis [see Warnings and Precautions (5.2)]
- Pancreatitis [see Warnings and Precautions (5.3)]
- Volume Depletion [see Warnings and Precautions (5.4)]
- Genitourinary Infections, including Urosepsis, Pyelonephritis, Necrotizing Fasciitis of the Perineum (Fournier's Gangrene), and Genital Mycotic Infections [see Warnings and Precautions (5.5)]
- Hypoglycemia with Concomitant Use with Insulin and Insulin Secretagogues [see Warnings and Precautions (5.6)]
- Lower Limb Amputation [see Warnings and Precautions (5.7)]
- Hypersensitivity Reactions [see Warnings and Precautions (5.8)]
- Vitamin B12 Deficiency [see Warnings and Precautions (5.9)]
- Severe and Disabling Arthralgia [see Warnings and Precautions (5.10)]
- Bullous Pemphigoid [see Warnings and Precautions (5.11)]
- Heart Failure [see Warnings and Precautions (5.12)]

6.1 Clinical Trials Experience

Because clinical trials are conducted under widely varying conditions, adverse reaction rates observed in the clinical trials of a drug cannot be directly compared to rates in the clinical trials of another drug and may not reflect the rates observed in practice.

Empagliflozin, Linagliptin and Metformin HCl

The safety of concomitantly administered empagliflozin (daily dosage 10 mg or 25 mg), linagliptin (daily dosage 5 mg) and metformin HCl has been evaluated in a total of 686 patients with type 2 diabetes mellitus treated for up to 52 weeks in an active-controlled clinical trial. The most common adverse reactions are shown in Table 1.

Table 1 Adverse Reactions Reported in ≥5% of Patients Treated with Empagliflozin, Linagliptin, and Metformin HCl in an Active-Controlled Clinical Trial of 52 Weeks
Adverse Reactions | Empagliflozin 10 mg + Linagliptin 5 mg + Metformin HCl (%) n=136 | Empagliflozin 25 mg + Linagliptin 5 mg + Metformin HCl (%) n=137
Upper respiratory tract infection | 10.3 | 8.0
Urinary tract infectiona | 9.6 | 10.2
Nasopharyngitis | 8.1 | 5.8
Diarrhea | 6.6 | 2.2
Constipation | 5.1 | 5.8
Headache | 5.1 | 5.1
Gastroenteritis | 2.9 | 5.8
aPredefined grouping, including, but not limited to, urinary tract infection, asymptomatic bacteriuria, cystitis

Hypoglycemia

The incidence of hypoglycemia (defined as plasma or capillary glucose of less than 54 mg/dL) was 0.7% in patients receiving empagliflozin 10 mg/linagliptin 5 mg/metformin HCl and 0.7% in patients receiving empagliflozin 25 mg/linagliptin 5 mg/metformin HCl. Events of severe hypoglycemia (requiring assistance regardless of blood glucose) did not occur in this trial.

Empagliflozin

Adverse reactions that occurred in ≥2% of patients receiving empagliflozin and more commonly than in patients given placebo included (10 mg, 25 mg, and placebo): urinary tract infection (9.3%, 7.6%, and 7.6%), female genital mycotic infections (5.4%, 6.4%, and 1.5%), upper respiratory tract infection (3.1%, 4.0%, and 3.8%), increased urination (3.4%, 3.2%, and 1.0%), dyslipidemia (3.9%, 2.9%, and 3.4%), arthralgia (2.4%, 2.3%, and 2.2%), male genital mycotic infections (3.1%, 1.6%, and 0.4%), and nausea (2.3%, 1.1%, and 1.4%).

Thirst (including polydipsia) was reported in 0%, 1.7%, and 1.5% for placebo, empagliflozin 10 mg, and empagliflozin 25 mg, respectively.

Empagliflozin causes an osmotic diuresis, which may lead to intravascular volume contraction and adverse reactions related to volume depletion. Events related to volume depletion (hypotension and syncope) were reported in 3 patients (1.1%) treated with empagliflozin, linagliptin and metformin HCl combination therapy.

Linagliptin

Adverse reactions reported in ≥2% of patients treated with linagliptin 5 mg and more commonly than in patients treated with placebo included: nasopharyngitis (7.0% and 6.1%), diarrhea (3.3% and 3.0%), and cough (2.1% and 1.4%).

Other adverse reactions reported in clinical trials with treatment of linagliptin monotherapy were hypersensitivity (e.g., urticaria, angioedema, localized skin exfoliation, or bronchial hyperreactivity) and myalgia.

In the clinical trial program, pancreatitis was reported in 15.2 cases per 10,000 patient-year exposure while being treated with linagliptin, compared with 3.7 cases per 10,000 patient-year exposure while being treated with comparator (placebo and active comparator, sulfonylurea). Three additional cases of pancreatitis were reported following the last administered dose of linagliptin.

Metformin HCl

The most common (>5%) adverse reactions due to initiation of metformin HCl therapy are diarrhea, nausea/vomiting, flatulence, abdominal discomfort, indigestion, asthenia, and headache.

In a 24-week clinical trial in which extended-release metformin HCl or placebo was added to glyburide therapy, the most common (>5% and greater than placebo) adverse reactions in the combined treatment group were hypoglycemia (13.7% vs 4.9%), diarrhea (12.5% vs 5.6%), and nausea (6.7% vs 4.2%).

Other Adverse Reactions in Clinical Trials with Empagliflozin in Adults

- Genital Mycotic Infections: In the pool of five placebo-controlled clinical trials, the incidence of genital mycotic infections (e.g., vaginal mycotic infection, vaginal infection, genital infection fungal, vulvovaginal candidiasis, and vulvitis) was increased in patients treated with empagliflozin compared to placebo, occurring in 0.9%, 4.1%, and 3.7% of patients randomized to placebo, empagliflozin 10 mg, and empagliflozin 25 mg, respectively. Discontinuation from trial due to genital infection occurred in 0% of placebo-treated patients and 0.2% of patients treated with either empagliflozin 10 mg or 25 mg.
  Genital mycotic infections occurred more frequently in female than male patients.
  Phimosis occurred more frequently in male patients treated with empagliflozin 10 mg (less than 0.1%) and empagliflozin 25 mg (0.1%) than placebo (0%).
- Urinary Tract Infections: In the pool of five placebo-controlled clinical trials, the incidence of urinary tract infections (e.g., urinary tract infection, asymptomatic bacteriuria, and cystitis) was increased in patients treated with empagliflozin compared to placebo. Patients with a history of chronic or recurrent urinary tract infections were more likely to experience a urinary tract infection. The rate of treatment discontinuation due to urinary tract infections was 0.1%, 0.2%, and 0.1% for placebo, empagliflozin 10 mg, and empagliflozin 25 mg, respectively.
  Urinary tract infections occurred more frequently in female patients. The incidence of urinary tract infections in female patients randomized to placebo, empagliflozin 10 mg, and empagliflozin 25 mg was 16.6%, 18.4%, and 17.0%, respectively. The incidence of urinary tract infections in male patients randomized to placebo, empagliflozin 10 mg, and empagliflozin 25 mg was 3.2%, 3.6%, and 4.1%, respectively [see Use in Specific Populations (8.5)].
- Lower Limb Amputations: Across four empagliflozin outcome trials, lower limb amputation event rates were 4.3 and 5.0 events per 1,000 patient-years in the placebo group and the empagliflozin 10 mg or 25 mg dose group, respectively, with a HR of 1.05 (95% CI) (0.81, 1.36). In a long-term cardio-renal outcome trial with empagliflozin, in patients with chronic kidney disease, the occurrence of lower limb amputations was reported with event rates of 2.9, and 4.3 events per 1,000 patient-years in the placebo, and empagliflozin 10 mg treatment arms, respectively. TRIJARDY XR is not indicated for the treatment of chronic kidney disease.

Laboratory Test Abnormalities in Clinical Trials of Empagliflozin, Linagliptin, or Metformin HCl

Empagliflozin

Increases in Serum Creatinine and Decreases in eGFR: Initiation of empagliflozin causes an increase in serum creatinine and decrease in eGFR within weeks of starting therapy and then these changes stabilize. In a trial of patients with moderate renal impairment, larger mean changes were observed. In a long-term CV outcomes trial, the increase in serum creatinine and decrease in eGFR generally did not exceed 0.1 mg/dL and -9.0 mL/min/1.73 m^2, respectively, at Week 4, and reversed after treatment discontinuation, suggesting acute hemodynamic changes may play a role in the renal function changes observed with empagliflozin.

Increase in Low-Density Lipoprotein Cholesterol (LDL-C): Dose-related increases in low-density lipoprotein cholesterol (LDL-C) were observed in patients treated with empagliflozin. LDL-C increased by 2.3%, 4.6%, and 6.5% in patients treated with placebo, empagliflozin 10 mg, and empagliflozin 25 mg, respectively. The range of mean baseline LDL-C levels was 90.3 to 90.6 mg/dL across treatment groups.

Increase in Hematocrit: Median hematocrit decreased by 1.3% in placebo and increased by 2.8% in empagliflozin 10 mg and 2.8% in empagliflozin 25 mg-treated patients. At the end of treatment, 0.6%, 2.7%, and 3.5% of patients with hematocrits initially within the reference range had values above the upper limit of the reference range with placebo, empagliflozin 10 mg, and empagliflozin 25 mg, respectively.

Linagliptin

Increase in Uric Acid: Changes in laboratory values that occurred more frequently in the linagliptin group and ≥1% more than in the placebo group were increases in uric acid (1.3% in the placebo group, 2.7% in the linagliptin group).

Increase in Lipase: In a placebo-controlled clinical trial with linagliptin in type 2 diabetes mellitus patients with micro- or macroalbuminuria, a mean increase of 30% in lipase concentrations from baseline to 24 weeks was observed in the linagliptin arm, compared to a mean decrease of 2% in the placebo arm. Lipase levels above 3 times upper limit of normal were seen in 8.2% compared to 1.7% patients in the linagliptin and placebo arms, respectively.

Increase in Amylase: In a CV safety trial comparing linagliptin versus glimepiride in patients with type 2 diabetes mellitus, amylase levels above 3 times upper limit of normal were seen in 1.0% compared to 0.5% of patients in the linagliptin and glimepiride arms, respectively.

The clinical significance of elevations in lipase and amylase with linagliptin is unknown in the absence of other signs and symptoms of pancreatitis [see Warnings and Precautions (5.3)].

Metformin HCl

Decrease in Vitamin B12: In metformin HCl clinical trials of 29-week duration, a decrease to subnormal levels of previously normal serum vitamin B12 levels was observed in approximately 7% of patients.

6.2 Postmarketing Experience

Additional adverse reactions have been identified during postapproval use of linagliptin, empagliflozin, or metformin HCl. Because these reactions are reported voluntarily from a population of uncertain size, it is generally not possible to reliably estimate their frequency or establish a causal relationship to drug exposure.

- Gastrointestinal Disorders: Acute pancreatitis, including fatal pancreatitis [see Indications and Usage (1)], mouth ulceration, stomatitis
- Immune System Disorders: Hypersensitivity reactions including anaphylaxis, angioedema, and exfoliative skin conditions
- Infections: Necrotizing fasciitis of the perineum (Fournier's gangrene), urosepsis and pyelonephritis
- Metabolism and Nutrition Disorders: Ketoacidosis
- Musculoskeletal and Connective Tissue Disorders: Rhabdomyolysis, severe and disabling arthralgia
- Renal and Urinary Disorders: Acute kidney injury
- Skin and Subcutaneous Tissue Disorders: Bullous pemphigoid, skin reactions (e.g., rash, urticaria)
- Hepatobiliary Disorders: Cholestatic, hepatocellular, and mixed hepatocellular liver injury

7 DRUG INTERACTIONS

Table 2 describes clinically relevant interactions with TRIJARDY XR.

Table 2 Clinically Relevant Interactions with TRIJARDY XR
Carbonic Anhydrase Inhibitors
Clinical Impact | Topiramate or other carbonic anhydrase inhibitors (e.g., zonisamide, acetazolamide or dichlorphenamide) frequently causes a decrease in serum bicarbonate and induce non-anion gap, hyperchloremic metabolic acidosis. Concomitant use of these drugs with TRIJARDY XR may increase the risk of lactic acidosis.
Intervention | Consider more frequent monitoring of these patients.
Drugs that Reduce Metformin Clearance
Clinical Impact | Concomitant use of drugs that interfere with common renal tubular transport systems involved in the renal elimination of metformin (e.g., organic cationic transporter-2 [OCT2] / multidrug and toxin extrusion [MATE] inhibitors such as ranolazine, vandetanib, dolutegravir, and cimetidine) could increase systemic exposure to metformin and may increase the risk for lactic acidosis [see Clinical Pharmacology (12.3)].
Intervention | Consider the benefits and risks of concomitant use.
Alcohol
Clinical Impact | Alcohol is known to potentiate the effect of metformin on lactate metabolism.
Intervention | Warn patients against excessive alcohol intake while receiving TRIJARDY XR.
Diuretics
Clinical Impact | Coadministration of empagliflozin with diuretics resulted in increased urine volume and frequency of voids, which might enhance the potential for volume depletion.
Intervention | Before initiating TRIJARDY XR, assess volume status and renal function. In patients with volume depletion, correct this condition before initiating TRIJARDY XR. Monitor for signs and symptoms of volume depletion, and renal function after initiating therapy.
Insulin or Insulin Secretagogues
Clinical Impact | The risk of hypoglycemia is increased when TRIJARDY XR is used in combination with an insulin secretagogue (e.g., sulfonylurea) or insulin.
Intervention | Coadministration of TRIJARDY XR with an insulin secretagogue (e.g., sulfonylurea) or insulin may require lower dosages of the insulin secretagogue or insulin to reduce the risk of hypoglycemia.
Drugs Affecting Glycemic Control
Clinical Impact | Certain drugs tend to produce hyperglycemia and may lead to loss of glycemic control. These drugs include the thiazides and other diuretics, corticosteroids, phenothiazines, thyroid products, estrogens, oral contraceptives, phenytoin, nicotinic acid, sympathomimetics, calcium channel blocking drugs, and isoniazid.
Intervention | When such drugs are administered to a patient receiving TRIJARDY XR, the patient should be closely observed to maintain adequate glycemic control. When such drugs are withdrawn from a patient receiving TRIJARDY XR, the patient should be observed closely for hypoglycemia.
Lithium
Clinical Impact | Concomitant use of an SGLT2 inhibitor with lithium may decrease serum lithium concentrations.
Intervention | Monitor serum lithium concentration more frequently during TRIJARDY XR initiation and dosage changes.
Inducers of P-glycoprotein or CYP3A4 Enzymes
Clinical Impact | Rifampin decreased linagliptin exposure, suggesting that the efficacy of linagliptin may be reduced when administered in combination with a strong P-gp or CYP3A4 inducer.
Intervention | Use of alternative treatments is strongly recommended when linagliptin is to be administered with a strong P-gp or CYP3A4 inducer.
Positive Urine Glucose Test
Clinical Impact | SGLT2 inhibitors increase urinary glucose excretion and will lead to positive urine glucose tests.
Intervention | Monitoring glycemic control with urine glucose tests is not recommended in patients taking SGLT2 inhibitors. Use alternative methods to monitor glycemic control.
Interference with 1,5-anhydroglucitol (1,5-AG) Assay
Clinical Impact | Measurements of 1,5-AG are unreliable in assessing glycemic control in patients taking SGLT2 inhibitors.
Intervention | Monitoring glycemic control with 1,5-AG assay is not recommended. Use alternative methods to monitor glycemic control.

8 USE IN SPECIFIC POPULATIONS

8.1 Pregnancy

Risk Summary

Based on animal data showing adverse renal effects from empagliflozin, TRIJARDY XR is not recommended during the second and third trimesters of pregnancy.

The limited available data with TRIJARDY XR, linagliptin, or empagliflozin in pregnant women are not sufficient to determine a drug-associated risk for major birth defects and miscarriage. Published studies with metformin HCl use during pregnancy have not reported a clear association with metformin HCl and major birth defect or miscarriage risk (see Data). There are risks to the mother and fetus associated with poorly controlled diabetes in pregnancy (see Clinical Considerations).

In animal studies, empagliflozin, a component of TRIJARDY XR, resulted in adverse renal changes in rats when administered during a period of renal development corresponding to the late second and third trimesters of human pregnancy. Doses approximately 13-times the maximum clinical dose caused renal pelvic and tubule dilatations that were reversible. No adverse developmental effects were observed when linagliptin or metformin HCl were administered to pregnant rats or rabbits (see Data).

The estimated background risk of major birth defects is 6% to 10% in women with pre-gestational diabetes with a HbA1c >7 and has been reported to be as high as 20% to 25% in women with HbA1c >10. The estimated background risk of miscarriage for the indicated population is unknown. In the U.S. general population, the estimated background risk of major birth defects and miscarriage in clinically recognized pregnancies is 2% to 4% and 15% to 20%, respectively.

Clinical Considerations

Disease-associated maternal and/or embryo/fetal risk

Poorly controlled diabetes in pregnancy increases the maternal risk for diabetic ketoacidosis, pre-eclampsia, spontaneous abortions, preterm delivery, and delivery complications. Poorly controlled diabetes increases the fetal risk for major birth defects, stillbirth, and macrosomia related morbidity.

Data

Human Data

Published data from postmarketing studies have not reported a clear association with metformin HCl and major birth defects, miscarriage, or adverse maternal or fetal outcomes when metformin HCl was used during pregnancy. However, these studies cannot definitely establish the absence of any metformin-associated risk because of methodological limitations, including small sample size and inconsistent comparator groups.

Animal Data

Empagliflozin: Empagliflozin dosed directly to juvenile rats from postnatal day (PND) 21 until PND 90 at doses of 1, 10, 30, and 100 mg/kg/day caused increased kidney weights and renal tubular and pelvic dilatation at 100 mg/kg/day, which approximates 13-times the maximum clinical dose of 25 mg, based on AUC. These findings were not observed after a 13-week, drug-free recovery period. These outcomes occurred with drug exposure during periods of renal development in rats that correspond to the late second and third trimester of human renal development.

In embryo-fetal development studies in rats and rabbits, empagliflozin was administered for intervals coinciding with the first trimester period of organogenesis in humans. Doses up to 300 mg/kg/day, which approximates 48-times (rats) and 128-times (rabbits) the maximum clinical dose of 25 mg (based on AUC), did not result in adverse developmental effects. In rats, at higher doses of empagliflozin causing maternal toxicity, malformations of limb bones increased in fetuses at 700 mg/kg/day or 154-times the 25 mg maximum clinical dose. Empagliflozin crosses the placenta and reaches fetal tissues in rats. In the rabbit, higher doses of empagliflozin resulted in maternal and fetal toxicity at 700 mg/kg/day, or 139-times the 25 mg maximum clinical dose.

In pre- and postnatal development studies in pregnant rats, empagliflozin was administered from gestation day 6 through to lactation day 20 (weaning) at up to 100 mg/kg/day (approximately 16-times the 25 mg maximum clinical dose) without maternal toxicity. Reduced body weight was observed in the offspring at greater than or equal to 30 mg/kg/day (approximately 4-times the 25 mg maximum clinical dose).

Linagliptin: No adverse developmental outcome was observed when linagliptin was administered to pregnant Wistar Han rats and Himalayan rabbits during the period of organogenesis at doses up to 240 mg/kg/day and 150 mg/kg/day, respectively. These doses represent approximately 943-times (rats) and 1,943-times (rabbits) the 5 mg maximum clinical dose, based on exposure. No adverse functional, behavioral, or reproductive outcome was observed in offspring following administration of linagliptin to Wistar Han rats from gestation day 6 to lactation day 21 at a dose 49-times the maximum recommended human dose, based on exposure.

Linagliptin crosses the placenta into the fetus following oral dosing in pregnant rats and rabbits.

Metformin HCl: Metformin HCl did not cause adverse developmental effects when administered to pregnant Sprague Dawley rats and rabbits at doses up to 600 mg/kg/day during the period of organogenesis. This represents an exposure of approximately 2- and 6-times a clinical dose of 2,000 mg, based on body surface area (mg/m^2) for rats and rabbits, respectively.

8.2 Lactation

Risk Summary

There is limited information regarding the presence of TRIJARDY XR, or its components (empagliflozin, linagliptin, or metformin HCl) in human milk, the effects on the breastfed infant, or the effects on milk production. Limited published studies report that metformin is present in human milk (see Data). Empagliflozin and linagliptin are present in rat milk (see Data). Since human kidney maturation occurs in utero and during the first 2 years of life when lactational exposure may occur, there may be risk to the developing human kidney.

Because of the potential for serious adverse reactions in a breastfed infant, including the potential for empagliflozin to affect postnatal renal development, advise patients that use of TRIJARDY XR is not recommended while breastfeeding.

Data

Published clinical lactation studies report that metformin is present in human milk which resulted in infant doses approximately 0.11% to 1% of the maternal weight-adjusted dosage and a milk/plasma ratio ranging between 0.13 and 1. However, the studies were not designed to definitely establish the risk of use of metformin HCl during lactation because of small sample size and limited adverse event data collected in infants.

Empagliflozin was present at a low level in rat fetal tissues after a single oral dose to the dams at gestation day 18. In rat milk, the mean milk to plasma ratio ranged from 0.634 to 5, and was greater than one from 2 to 24 hours post-dose. The mean maximal milk to plasma ratio of 5 occurred at 8 hours post-dose, suggesting accumulation of empagliflozin in the milk. Juvenile rats directly exposed to empagliflozin showed a risk to the developing kidney (renal pelvic and tubular dilatations) during maturation.

8.3 Females and Males of Reproductive Potential

Discuss the potential for unintended pregnancy with premenopausal women as therapy with metformin HCl may result in ovulation in some anovulatory women.

8.4 Pediatric Use

Safety and effectiveness of TRIJARDY XR have not been established in pediatric patients.

8.5 Geriatric Use

Assess renal function more frequently in TRIJARDY XR-treated geriatric patients because there is a greater risk of empagliflozin-associated intravascular volume contraction and symptomatic hypotension in geriatric patients and there is a greater risk of metformin-associated lactic acidosis in geriatric patients [see Warnings and Precautions (5.1, 5.4)].

The recommended dosage for the metformin HCl component of TRIJARDY XR in geriatric patients should usually start at the lower end of the dosage range.

Of the 273 patients treated with the combination of empagliflozin, linagliptin, and metformin HCl to improve glycemic control in adults with type 2 diabetes mellitus, 58 were 65 years of age and older, while 8 were 75 years of age and older. Clinical trials of TRIJARDY XR did not include sufficient numbers of geriatric patients to determine whether they respond differently from younger adult patients.

Empagliflozin

In empagliflozin type 2 diabetes mellitus trials, 2,721 empagliflozin-treated patients were 65 years of age and older and 491 patients were 75 years of age and older. In these trials, volume depletion-related adverse reactions occurred in 2.1%, 2.3%, and 4.4% of patients 75 years of age and older in the placebo, empagliflozin 10 mg, and empagliflozin 25 mg once daily groups, respectively; and urinary tract infections occurred in 10.5%, 15.7%, and 15.1% of patients 75 years of age and older in the placebo, empagliflozin 10 mg, and empagliflozin 25 mg once daily groups, respectively.

Linagliptin

In linagliptin trials, 1,085 linagliptin-treated patients were 65 years of age and older and 131 patients were 75 years of age and older. In these linagliptin trials, no overall differences in safety or effectiveness of linagliptin were observed between geriatric patients and younger adult patients.

Metformin HCl

Clinical trials of metformin HCl did not include sufficient numbers of patients 65 years of age and older to determine whether they respond differently from younger adult patients.

8.6 Renal Impairment

TRIJARDY XR should not be initiated in patients with an eGFR less than 45 mL/min/1.73 m^2 due to the metformin HCl component and is contraindicated in patients with severe renal impairment (eGFR less than 30 mL/min/1.73 m^2).

Empagliflozin

The glucose lowering benefit of empagliflozin 25 mg decreased in patients with worsening renal function. The risks of renal impairment [see Warnings and Precautions (5.4)], volume depletion adverse reactions and urinary tract infection-related adverse reactions increased with worsening renal function.

Metformin HCl

Metformin is substantially excreted by the kidney, and the risk of metformin accumulation and lactic acidosis increases with the degree of renal impairment [see Warnings and Precautions (5.1)].

8.7 Hepatic Impairment

Use of metformin HCl in patients with hepatic impairment has been associated with some cases of lactic acidosis. TRIJARDY XR is not recommended in patients with hepatic impairment [see Warnings and Precautions (5.1)].

10 OVERDOSAGE

In the event of an overdose with TRIJARDY XR, consider contacting the Poison Help line (1-800-222-1222) or a medical toxicologist for additional overdosage management recommendations.

Overdose of metformin HCl has occurred, including ingestion of amounts greater than 50 grams. Lactic acidosis has been reported in approximately 32% of metformin overdose cases [see Warnings and Precautions (5.1)]. Metformin is dialyzable with a clearance of up to 170 mL/min under good hemodynamic conditions. Therefore, hemodialysis may be useful for removal of accumulated drug from patients in whom metformin overdosage is suspected.

Removal of empagliflozin by hemodialysis has not been studied, and removal of linagliptin by hemodialysis or peritoneal dialysis is unlikely.

11 DESCRIPTION

TRIJARDY XR tablets for oral use contain: empagliflozin, linagliptin, and metformin HCl.

Empagliflozin

Empagliflozin is an inhibitor of the SGLT2.

The chemical name of empagliflozin is D-Glucitol,1,5-anhydro-1-C-[4-chloro-3-[[4-[[(3S)-tetrahydro-3-furanyl]oxy]phenyl]methyl]phenyl]-, (1S).

The molecular formula is C23H27ClO7 and the molecular weight is 450.91. The structural formula is:

Empagliflozin is a white to yellowish, non-hygroscopic powder. It is very slightly soluble in water, sparingly soluble in methanol, slightly soluble in ethanol and acetonitrile, soluble in 50% acetonitrile/water, and practically insoluble in toluene.

Linagliptin

Linagliptin is an inhibitor of the DPP-4 enzyme.

The chemical name of linagliptin is 1H-Purine-2,6-dione, 8-[(3R)-3-amino-1-piperidinyl]-7-(2-butyn-1-yl)-3,7-dihydro-3-methyl-1-[(4-methyl-2-quinazolinyl)methyl]-

The molecular formula is C25H28N8O2 and the molecular weight is 472.54. The structural formula is:

Linagliptin is a white to yellowish, not or only slightly hygroscopic solid substance. It is very slightly soluble in water. Linagliptin is soluble in methanol, sparingly soluble in ethanol, very slightly soluble in isopropanol, and very slightly soluble in acetone.

Metformin HCl

Metformin HCl (N,N-dimethylimidodicarbonimidic diamide hydrochloride) is a biguanide. Metformin HCl is a white to off-white crystalline compound with a molecular formula of C4H11N5∙HCl and a molecular weight of 165.63. Metformin HCl is freely soluble in water and is practically insoluble in acetone, ether, and chloroform. The pKa of metformin is 12.4. The pH of a 1% aqueous solution of metformin hydrochloride is 6.68. The structural formula is:

TRIJARDY XR

Each film-coated tablet of TRIJARDY XR consists of an extended-release metformin HCl core tablet that is coated with the immediate-release drug substances: empagliflozin and linagliptin.

TRIJARDY XR tablets for oral administration are available in four strengths containing:

- 5 mg empagliflozin, 2.5 mg linagliptin, and 1,000 mg metformin HCl (equivalent to 779.86 mg of metformin)
- 10 mg empagliflozin, 5 mg linagliptin, and 1,000 mg metformin HCl (equivalent to 779.86 mg of metformin)
- 12.5 mg empagliflozin, 2.5 mg linagliptin, and 1,000 mg metformin HCl (equivalent to 779.86 mg of metformin)
- 25 mg empagliflozin, 5 mg linagliptin, and 1,000 mg metformin HCl (equivalent to 779.86 mg of metformin)

Each film-coated tablet of TRIJARDY XR contains the following inactive ingredients: Tablet Core: hypromellose, magnesium stearate, and polyethylene oxide. Film Coatings and Printing Ink: ammonium hydroxide, arginine, carnauba wax, ferric oxide yellow and ferric oxide red (10 mg/5 mg/1,000 mg), ferrosoferric oxide and ferric oxide red (12.5 mg/2.5 mg/1,000 mg), ferrosoferric oxide and ferric oxide yellow (5 mg/2.5 mg/1,000 mg and 25 mg/5 mg/1,000 mg), hydroxypropyl cellulose, hypromellose, isopropyl alcohol, n-butyl alcohol, polyethylene glycol, propylene glycol, purified water, shellac glaze, talc, and titanium dioxide.

12 CLINICAL PHARMACOLOGY

12.1 Mechanism of Action

TRIJARDY XR

TRIJARDY XR contains: empagliflozin, a SGLT2 inhibitor, linagliptin, a DPP-4 inhibitor, and metformin HCl, a biguanide.

Empagliflozin

Empagliflozin is an inhibitor of SGLT2, the predominant transporter responsible for reabsorption of glucose from the glomerular filtrate back into the circulation. By inhibiting SGLT2, empagliflozin reduces renal reabsorption of filtered glucose and lowers the renal threshold for glucose, and thereby increases urinary glucose excretion.

Linagliptin

Linagliptin is an inhibitor of DPP-4, an enzyme that degrades the incretin hormones glucagon-like peptide-1 (GLP-1) and glucose-dependent insulinotropic polypeptide (GIP). Thus, linagliptin increases the concentrations of active incretin hormones, stimulating the release of insulin in a glucose-dependent manner and decreasing the levels of glucagon in the circulation. Both incretin hormones are involved in the physiological regulation of glucose homeostasis. Incretin hormones are secreted at a low basal level throughout the day and levels rise immediately after meal intake. GLP-1 and GIP increase insulin biosynthesis and secretion from pancreatic beta cells in the presence of normal and elevated blood glucose levels. Furthermore, GLP-1 also reduces glucagon secretion from pancreatic alpha cells, resulting in a reduction in hepatic glucose output.

Metformin HCl

Metformin HCl is an antihyperglycemic agent which improves glucose tolerance in patients with type 2 diabetes mellitus, lowering both basal and postprandial plasma glucose. Metformin HCl decreases hepatic glucose production, decreases intestinal absorption of glucose, and improves insulin sensitivity by increasing peripheral glucose uptake and utilization. With metformin HCl therapy, insulin secretion remains unchanged while fasting insulin levels and day-long plasma insulin response may decrease.

12.2 Pharmacodynamics

Empagliflozin

Urinary Glucose Excretion

In patients with type 2 diabetes mellitus, urinary glucose excretion increased immediately following a dose of empagliflozin and was maintained at the end of a 4-week treatment period averaging at approximately 64 grams per day with 10 mg empagliflozin and 78 grams per day with 25 mg empagliflozin once daily. Data from single oral doses of empagliflozin in healthy subjects indicate that, on average, the elevation in urinary glucose excretion approaches baseline by about 3 days for the 10 mg and 25 mg doses.

Urinary Volume

In a 5-day study, mean 24-hour urine volume increase from baseline was 341 mL on Day 1 and 135 mL on Day 5 of empagliflozin 25 mg once daily treatment.

Cardiac Electrophysiology

In a randomized, placebo-controlled, active-comparator, crossover study, 30 healthy subjects were administered a single oral dose of empagliflozin 25 mg, empagliflozin 200 mg (8 times the maximum recommended dose), moxifloxacin, and placebo. No increase in QTc was observed with either 25 mg or 200 mg empagliflozin.

Linagliptin

Linagliptin binds to DPP-4 in a reversible manner and increases the concentrations of incretin hormones. Linagliptin glucose-dependently increases insulin secretion and lowers glucagon secretion, thus resulting in a better regulation of the glucose homeostasis. Linagliptin binds selectively to DPP-4 and selectively inhibits DPP-4, but not DPP-8 or DPP-9 activity in vitro at concentrations approximating therapeutic exposures.

Cardiac Electrophysiology

In a randomized, placebo-controlled, active-comparator, 4-way crossover study, 36 healthy subjects were administered a single oral dose of linagliptin 5 mg, linagliptin 100 mg (20 times the recommended dose), moxifloxacin, and placebo. No increase in QTc was observed with either the recommended dose of 5 mg or the 100 mg dose. At the 100 mg dose, peak linagliptin plasma concentrations were approximately 38-fold higher than the peak concentrations following a 5-mg dose.

12.3 Pharmacokinetics

TRIJARDY XR

Administration of TRIJARDY XR with food resulted in no change in overall exposure of empagliflozin or linagliptin. For metformin HCl extended-release, high-fat meals increased systemic exposure (as measured by area-under-the-curve [AUC]) by approximately 70% relative to fasting, while Cmax is not affected. Meals prolonged Tmax by approximately 3 hours.

Empagliflozin

The pharmacokinetics of empagliflozin has been characterized in healthy volunteers and patients with type 2 diabetes mellitus and no clinically relevant differences were noted between the two populations. The steady-state mean plasma AUC and Cmax were 1,870 nmol∙h/L and 259 nmol/L, respectively, with 10 mg empagliflozin once daily treatment, and 4,740 nmol∙h/L and 687 nmol/L, respectively, with 25 mg empagliflozin once daily treatment. Systemic exposure of empagliflozin increased in a dose-proportional manner in the therapeutic dose range. Empagliflozin does not appear to have time-dependent pharmacokinetic characteristics. Following once-daily dosing, up to 22% accumulation, with respect to plasma AUC, was observed at steady-state.

Absorption

After oral administration, peak plasma concentrations of empagliflozin were reached at 1.5 hours post-dose. Administration of 25 mg empagliflozin after intake of a high-fat and high-calorie meal resulted in slightly lower exposure; AUC decreased by approximately 16% and Cmax decreased by approximately 37%, compared to fasted condition. The observed effect of food on empagliflozin pharmacokinetics was not considered clinically relevant and empagliflozin may be administered with or without food.

Distribution

The apparent steady-state volume of distribution was estimated to be 73.8 L based on a population pharmacokinetic analysis. Following administration of an oral [^14C]-empagliflozin solution to healthy subjects, the red blood cell partitioning was approximately 36.8% and plasma protein binding was 86.2%.

Elimination

The apparent terminal elimination half-life of empagliflozin was estimated to be 12.4 h and apparent oral clearance was 10.6 L/h based on the population pharmacokinetic analysis.

Metabolism

No major metabolites of empagliflozin were detected in human plasma and the most abundant metabolites were three glucuronide conjugates (2-O-, 3-O-, and 6-O-glucuronide). Systemic exposure of each metabolite was less than 10% of total drug-related material. In vitro studies suggested that the primary route of metabolism of empagliflozin in humans is glucuronidation by the uridine 5'-diphospho-glucuronosyltransferases UGT2B7, UGT1A3, UGT1A8, and UGT1A9.

Excretion

Following administration of an oral [^14C]-empagliflozin solution to healthy subjects, approximately 95.6% of the drug-related radioactivity was eliminated in feces (41.2%) or urine (54.4%). The majority of drug-related radioactivity recovered in feces was unchanged parent drug and approximately half of drug-related radioactivity excreted in urine was unchanged parent drug.

Linagliptin

Absorption

The absolute bioavailability of linagliptin is approximately 30%. A high-fat meal reduced Cmax by 15% and increased AUC by 4%; this effect is not clinically relevant. Linagliptin may be administered with or without food.

Distribution

The mean apparent volume of distribution at steady-state following a single intravenous dose of linagliptin 5 mg to healthy subjects is approximately 1,110 L, indicating that linagliptin extensively distributes to the tissues. Plasma protein binding of linagliptin is concentration-dependent, decreasing from about 99% at 1 nmol/L to 75% to 89% at ≥30 nmol/L, reflecting saturation of binding to DPP-4 with increasing concentration of linagliptin. At high concentrations, where DPP-4 is fully saturated, 70% to 80% of linagliptin remains bound to plasma proteins and 20% to 30% is unbound in plasma. Plasma binding is not altered in patients with renal or hepatic impairment.

Elimination

Linagliptin has a terminal half-life of about 200 hours at steady-state, though the accumulation half-life is about 11 hours. Renal clearance at steady-state was approximately 70 mL/min.

Metabolism

Following oral administration, the majority (about 90%) of linagliptin is excreted unchanged, indicating that metabolism represents a minor elimination pathway. A small fraction of absorbed linagliptin is metabolized to a pharmacologically inactive metabolite, which shows a steady-state exposure of 13.3% relative to linagliptin.

Excretion

Following administration of an oral [^14C]-linagliptin dose to healthy subjects, approximately 85% of the administered radioactivity was eliminated via the enterohepatic system (80%) or urine (5%) within 4 days of dosing.

Metformin HCl extended-release

Absorption

Following a single oral dose of 1,000 mg (2 × 500 mg tablets) metformin HCl extended-release after a meal, the time to reach maximum plasma metformin concentration (Tmax) is achieved at approximately 7 to 8 hours. In both single- and multiple-dose studies in healthy subjects, once daily 1,000 mg (2 × 500 mg tablets) dosing provides equivalent systemic exposure, as measured by AUC, and up to 35% higher Cmax of metformin relative to the immediate-release given as 500 mg twice daily.

Single oral doses of metformin HCl extended-release from 500 mg to 2,500 mg resulted in less than proportional increase in both AUC and Cmax. Low-fat and high-fat meals increased the systemic exposure (as measured by AUC) from metformin extended-release tablets by about 38% and 73%, respectively, relative to fasting. Both meals prolonged metformin Tmax by approximately 3 hours but Cmax, was not affected.

Distribution

The apparent volume of distribution (V/F) of metformin following single oral doses of immediate-release metformin HCl tablets 850 mg averaged 654±358 L. Metformin is negligibly bound to plasma proteins. Metformin partitions into erythrocytes, most likely as a function of time.

Elimination

Metformin has a plasma elimination half-life of approximately 6.2 hours. In blood, the elimination half-life is approximately 17.6 hours, suggesting that the erythrocyte mass may be a compartment of distribution.

Metabolism

Intravenous single-dose studies in normal subjects demonstrate that metformin does not undergo hepatic metabolism (no metabolites have been identified in humans) nor biliary excretion.

Excretion

Following oral administration, approximately 90% of the absorbed drug is excreted via the renal route within the first 24 hours. Renal clearance is approximately 3.5 times greater than creatinine clearance, which indicates that tubular secretion is the major route of metformin elimination.

Specific Populations

Geriatric Patients

Empagliflozin: Age did not have a clinically meaningful impact on the pharmacokinetics of empagliflozin based on a population pharmacokinetic analysis [see Use in Specific Populations (8.5)].

Metformin HCl: Limited data from controlled pharmacokinetic studies of metformin HCl in healthy elderly subjects suggest that total plasma clearance of metformin is decreased, the half-life is prolonged, and Cmax is increased, compared with healthy young subjects. From these data, it appears that the change in metformin pharmacokinetics with aging is primarily accounted for by a change in renal function.

Effects of Age, Body Mass Index, Gender, and Race

Empagliflozin: Age, body mass index (BMI), gender and race (Asians versus primarily Whites) do not have a clinically meaningful effect on pharmacokinetics of empagliflozin.

Linagliptin: Based on the population PK analysis, age, body mass index (BMI), gender and race do not have a clinically meaningful effect on pharmacokinetics of linagliptin [see Use in Specific Populations (8.5)].

Metformin HCl: Metformin pharmacokinetic parameters did not differ significantly between normal subjects and patients with type 2 diabetes mellitus when analyzed according to gender. Similarly, in controlled clinical studies in patients with type 2 diabetes mellitus, the antihyperglycemic effect of metformin HCl was comparable in males and females.

No studies of metformin pharmacokinetic parameters according to race have been performed. In controlled clinical studies of metformin HCl in patients with type 2 diabetes mellitus, the antihyperglycemic effect was comparable in Whites (n=249), Blacks or African Americans (n=51), and Hispanics or Latinos (n=24).

Patients with Renal Impairment

TRIJARDY XR: Studies characterizing the pharmacokinetics of empagliflozin, linagliptin, and metformin HCl after administration of TRIJARDY XR in renally impaired patients have not been performed.

Empagliflozin: In patients with mild (eGFR: 60 to less than 90 mL/min/1.73 m^2), moderate (eGFR: 30 to less than 60 mL/min/1.73 m^2), and severe (eGFR: less than 30 mL/min/1.73 m^2) renal impairment and patients on dialysis due to kidney failure, AUC of empagliflozin increased by approximately 18%, 20%, 66%, and 48%, respectively, compared to subjects with normal renal function. Peak plasma levels of empagliflozin were similar in patients with moderate renal impairment and patients on dialysis due to kidney failure compared to subjects with normal renal function. Peak plasma levels of empagliflozin were roughly 20% higher in patients with mild and severe renal impairment, as compared to subjects with normal renal function. Population pharmacokinetic analysis showed that the apparent oral clearance of empagliflozin decreased, with a decrease in eGFR leading to an increase in drug exposure. However, the fraction of empagliflozin that was excreted unchanged in urine, and urinary glucose excretion, declined with decrease in eGFR.

Linagliptin: An open-label pharmacokinetic study evaluated the pharmacokinetics of linagliptin 5 mg in male and female patients with varying degrees of chronic renal impairment. The study included 6 healthy subjects with normal renal function (creatinine clearance [CrCl] ≥80 mL/min), 6 patients with mild renal impairment (CrCl 50 to <80 mL/min), 6 patients with moderate renal impairment (CrCl 30 to <50 mL/min), 10 patients with type 2 diabetes mellitus and severe renal impairment (CrCl <30 mL/min), and 11 patients with type 2 diabetes mellitus and normal renal function. Creatinine clearance was measured by 24-hour urinary creatinine clearance measurements or estimated from serum creatinine based on the Cockcroft-Gault formula.

Under steady-state conditions, linagliptin exposure in patients with mild renal impairment was comparable to healthy subjects.

In patients with moderate renal impairment under steady-state conditions, mean exposure of linagliptin increased (AUCτ,ss by 71% and Cmax by 46%), compared with healthy subjects. This increase was not associated with a prolonged accumulation half-life, terminal half-life, or an increased accumulation factor. Renal excretion of linagliptin was below 5% of the administered dose and was not affected by decreased renal function. Patients with type 2 diabetes mellitus and severe renal impairment showed steady-state exposure approximately 40% higher than that of patients with type 2 diabetes mellitus and normal renal function (increase in AUCτ,ss by 42% and Cmax by 35%). For both type 2 diabetes mellitus groups, renal excretion was below 7% of the administered dose.

These findings were further supported by the results of population pharmacokinetic analyses.

Metformin HCl: In patients with decreased renal function, the plasma and blood half-life of metformin is prolonged and the renal clearance is decreased [see Contraindications (4) and Warnings and Precautions (5.1)].

Patients with Hepatic Impairment

TRIJARDY XR: Studies characterizing the pharmacokinetics of empagliflozin, linagliptin, and metformin after administration of TRIJARDY XR in hepatically impaired patients have not been performed.

Empagliflozin: In patients with mild, moderate, and severe hepatic impairment according to the Child-Pugh classification, AUC of empagliflozin increased by approximately 23%, 47%, and 75% and Cmax increased by approximately 4%, 23%, and 48%, respectively, compared to subjects with normal hepatic function.

Linagliptin: In patients with mild hepatic impairment (Child-Pugh class A) steady-state exposure (AUCτ,ss) of linagliptin was approximately 25% lower and Cmax,ss was approximately 36% lower than in healthy subjects. In patients with moderate hepatic impairment (Child-Pugh class B), AUCss of linagliptin was about 14% lower and Cmax,ss was approximately 8% lower than in healthy subjects. Patients with severe hepatic impairment (Child-Pugh class C) had comparable exposure of linagliptin in terms of AUC0-24 and approximately 23% lower Cmax compared with healthy subjects. Reductions in the pharmacokinetic parameters seen in patients with hepatic impairment did not result in reductions in DPP-4 inhibition.

Metformin HCl: No pharmacokinetic studies of metformin have been conducted in patients with hepatic impairment.

Drug Interaction Studies

Pharmacokinetic drug interaction studies with TRIJARDY XR have not been performed; however, such studies have been conducted with the individual components of TRIJARDY XR (empagliflozin, linagliptin, and metformin HCl).

Empagliflozin

In vitro Assessment of Drug Interactions

Empagliflozin does not inhibit, inactivate, or induce CYP450 isoforms. In vitro data suggest that the primary route of metabolism of empagliflozin in humans is glucuronidation by the uridine 5'-diphospho-glucuronosyltransferases UGT1A3, UGT1A8, UGT1A9 and UGT2B7. Empagliflozin does not inhibit UGT1A1, UGT1A3, UGT1A8, UGT1A9, or UGT2B7. Therefore, no effect of empagliflozin is anticipated on concomitantly administered drugs that are substrates of the major CYP450 isoforms or UGT1A1, UGT1A3, UGT1A8, UGT1A9, or UGT2B7. The effect of UGT induction (e.g., induction by rifampicin or any other UGT enzyme inducer) on empagliflozin exposure has not been evaluated.

Empagliflozin is a substrate for P-glycoprotein (P-gp) and breast cancer resistance protein (BCRP), but it does not inhibit these efflux transporters at therapeutic doses. Based on in vitro studies, empagliflozin is considered unlikely to cause interactions with drugs that are P-gp substrates. Empagliflozin is a substrate of the human uptake transporters OAT3, OATP1B1, and OATP1B3, but not OAT1 and OCT2. Empagliflozin does not inhibit any of these human uptake transporters at clinically relevant plasma concentrations and, therefore, no effect of empagliflozin is anticipated on concomitantly administered drugs that are substrates of these uptake transporters.

In vivo Assessment of Drug Interactions

Empagliflozin pharmacokinetics were similar with and without coadministration of metformin HCl, glimepiride, pioglitazone, sitagliptin, linagliptin, warfarin, verapamil, ramipril, and simvastatin in healthy volunteers and with or without coadministration of hydrochlorothiazide and torsemide in patients with type 2 diabetes mellitus (see Figure 1). In subjects with normal renal function, coadministration of empagliflozin with probenecid resulted in a 30% decrease in the fraction of empagliflozin excreted in urine without any effect on 24-hour urinary glucose excretion. The relevance of this observation to patients with renal impairment is unknown.

Figure 1 Effect of Various Medications on the Pharmacokinetics of Empagliflozin as Displayed as 90% Confidence Interval of Geometric Mean AUC and Cmax Ratios [reference lines indicate 100% (80% - 125%)]

aempagliflozin, 50 mg, once daily; bempagliflozin, 25 mg, single dose; cempagliflozin, 25 mg, once daily; dempagliflozin, 10 mg, single dose

Empagliflozin had no clinically relevant effect on the pharmacokinetics of metformin, glimepiride, pioglitazone, sitagliptin, linagliptin, warfarin, digoxin, ramipril, simvastatin, hydrochlorothiazide, torsemide, and oral contraceptives when coadministered in healthy volunteers (see Figure 2).

Figure 2 Effect of Empagliflozin on the Pharmacokinetics of Various Medications as Displayed as 90% Confidence Interval of Geometric Mean AUC and Cmax Ratios [reference lines indicate 100% (80% - 125%)]

aempagliflozin, 50 mg, once daily; bempagliflozin, 25 mg, once daily; cempagliflozin, 25 mg, single dose; dadministered as simvastatin; eadministered as warfarin racemic mixture; fadministered as Microgynon®; gadministered as ramipril

Linagliptin

In vitro Assessment of Drug Interactions

Linagliptin is a weak to moderate inhibitor of CYP isozyme CYP3A4 but does not inhibit other CYP isozymes and is not an inducer of CYP isozymes, including CYP1A2, 2A6, 2B6, 2C8, 2C9, 2C19, 2D6, 2E1, and 4A11.

Linagliptin is a P-glycoprotein (P-gp) substrate and inhibits P-gp mediated transport of digoxin at high concentrations. Based on these results, and in vivo drug interaction studies, linagliptin is considered unlikely to cause interactions with other P-gp substrates at therapeutic concentrations.

In vivo Assessment of Drug Interactions

Strong inducers of CYP3A4 or P-gp (e.g., rifampin) decrease exposure to linagliptin to subtherapeutic and likely ineffective concentrations [see Drug Interactions (7)]. In vivo studies indicated evidence of a low propensity for causing drug interactions with substrates of CYP3A4, CYP2C9, CYP2C8, P-gp and organic cationic transporter (OCT).

Table 3 describes the effect of coadministered drugs on systemic exposure of linagliptin.

Table 3 Effect of Coadministered Drugs on Systemic Exposure of Linagliptin
Coadministered Drug | Dosing of Coadministered Druga | Dosing of Linagliptina | Geometric Mean Ratio (ratio with/without coadministered drug) No effect=1.0
 |  |  | AUCd | Cmax
Metformin | 850 mg TID | 10 mg QD | 1.20 | 1.03
Glyburide | 1.75 mgc | 5 mg QD | 1.02 | 1.01
Pioglitazone | 45 mg QD | 10 mg QD | 1.13 | 1.07
Ritonavir | 200 mg BID | 5 mgc | 2.01 | 2.96
Rifampinb | 600 mg QD | 5 mg QD | 0.60 | 0.56
aMultiple dose (steady-state) unless otherwise noted
bFor information regarding clinical recommendations [see Drug Interactions (7)].
cSingle dose
dAUC = AUC (0 to 24 hours) for single dose treatments and AUC = AUC (TAU) for multiple-dose treatments
QD = once daily
BID = twice daily
TID = three times daily

Table 4 describes the effect of linagliptin on systemic exposure of coadministered drugs.

Table 4 Effect of Linagliptin on Systemic Exposure of Coadministered Drugs
Coadministered Drug | Dosing of Coadministered Druga | Dosing of Linagliptina | Geometric Mean Ratio (ratio with/without coadministered drug) No effect=1.0
 |  |  |  | AUCc | Cmax
Metformin | 850 mg TID | 10 mg QD | metformin | 1.01 | 0.89
Glyburide | 1.75 mgb | 5 mg QD | glyburide | 0.86 | 0.86
Pioglitazone | 45 mg QD | 10 mg QD | pioglitazone metabolite M-III metabolite M-IV | 0.94 0.98 1.04 | 0.86 0.96 1.05
Digoxin | 0.25 mg QD | 5 mg QD | digoxin | 1.02 | 0.94
Simvastatin | 40 mg QD | 10 mg QD | simvastatin simvastatin acid | 1.34 1.33 | 1.10 1.21
Warfarin | 10 mgb | 5 mg QD | R-warfarin S-warfarin INR PT | 0.99 1.03 0.93d 1.03d | 1.00 1.01 1.04d 1.15d
Ethinylestradiol and levonorgestrel | ethinylestradiol 0.03 mg and levonorgestrel 0.150 mg QD | 5 mg QD | ethinylestradiol levonorgestrel | 1.01 1.09 | 1.08 1.13
aMultiple dose (steady-state) unless otherwise noted
bSingle dose
cAUC = AUC (INF) for single dose treatments and AUC = AUC (TAU) for multiple-dose treatments
dAUC = AUC (0-168) and Cmax = Emax for pharmacodynamic end points
INR = International Normalized Ratio
PT = Prothrombin Time
QD = once daily
TID = three times daily

Metformin HCl

Table 5 describes the effect of coadministered drugs on plasma metformin systemic exposure.

Table 5 Effect of Coadministered Drugs on Plasma Metformin Systemic Exposure
Coadministered Drug | Dosing of Coadministered Drug* | Dosing of Metformin HCl* | Geometric Mean Ratio (ratio with/without coadministered drug) No effect=1.0
 |  |  |  | AUC† | Cmax
Glyburide | 5 mg | 500 mg≠ | metformin | 0.98‡ | 0.99‡
Furosemide | 40 mg | 850 mg | metformin | 1.09‡ | 1.22‡
Nifedipine | 10 mg | 850 mg | metformin | 1.16 | 1.21
Propranolol | 40 mg | 850 mg | metformin | 0.90 | 0.94
Ibuprofen | 400 mg | 850 mg | metformin | 1.05‡ | 1.07‡
Cationic drugs eliminated by renal tubular secretion may reduce metformin elimination [see Drug Interactions (7)].
Cimetidine | 400 mg | 850 mg | metformin | 1.40 | 1.61
Carbonic anhydrase inhibitors may cause metabolic acidosis [see Drug Interactions (7)].
Topiramate** | 100 mg | 500 mg | metformin | 1.25 | 1.17
*All metformin and coadministered drugs were given as single doses
†AUC = AUC (INF)
≠Metformin HCl extended-release tablets 500 mg
‡Ratio of arithmetic means
**At steady-state with topiramate 100 mg every 12 hours and metformin 500 mg every 12 hours; AUC = AUC (0-12 hours)

Table 6 describes the effect of metformin on coadministered drug systemic exposure.

Table 6 Effect of Metformin on Coadministered Drug Systemic Exposure
Coadministered Drug | Dosing of Coadministered Drug* | Dosing of Metformin HCl* | Geometric Mean Ratio (ratio with/without metformin) No effect=1.0
 |  |  |  | AUC† | Cmax
Glyburide | 5 mg | 500 mg§ | glyburide | 0.78‡ | 0.63‡
Furosemide | 40 mg | 850 mg | furosemide | 0.87‡ | 0.69‡
Nifedipine | 10 mg | 850 mg | nifedipine | 1.10§ | 1.08
Propranolol | 40 mg | 850 mg | propranolol | 1.01§ | 0.94
Ibuprofen | 400 mg | 850 mg | ibuprofen | 0.97¶ | 1.01¶
Cimetidine | 400 mg | 850 mg | cimetidine | 0.95§ | 1.01
*All metformin and coadministered drugs were given as single doses
†AUC = AUC (INF) unless otherwise noted
§AUC (0-24 hours) reported
‡Ratio of arithmetic means, p-value of difference <0.05
¶Ratio of arithmetic means

13 NONCLINICAL TOXICOLOGY

13.1 Carcinogenesis, Mutagenesis, Impairment of Fertility

TRIJARDY XR

No carcinogenicity, mutagenicity, or impairment of fertility studies have been conducted with the combination of empagliflozin, linagliptin, and metformin HCl.

Empagliflozin

Carcinogenesis was evaluated in 2-year studies conducted in CD-1 mice and Wistar rats. Empagliflozin did not increase the incidence of tumors in female rats dosed at 100, 300, or 700 mg/kg/day (up to 72 times the exposure from the maximum clinical dose of 25 mg). In male rats, hemangiomas of the mesenteric lymph node were increased significantly at 700 mg/kg/day or approximately 42 times the exposure from a 25 mg clinical dose. Empagliflozin did not increase the incidence of tumors in female mice dosed at 100, 300, or 1,000 mg/kg/day (up to 62 times the exposure from a 25 mg clinical dose). Renal tubule adenomas and carcinomas were observed in male mice at 1,000 mg/kg/day, which is approximately 45 times the exposure of the maximum clinical dose of 25 mg. These tumors may be associated with a metabolic pathway predominantly present in the male mouse kidney.

Empagliflozin was not mutagenic or clastogenic with or without metabolic activation in the in vitro Ames bacterial mutagenicity assay, the in vitro L5178Y tk+/- mouse lymphoma cell assay, and an in vivo micronucleus assay in rats.

Empagliflozin had no effects on mating, fertility or early embryonic development in treated male or female rats, up to the high dose of 700 mg/kg/day (approximately 155 times the 25 mg clinical dose in males and females, respectively).

Linagliptin

Linagliptin did not increase the incidence of tumors in male and female rats in a 2-year study at doses of 6, 18, and 60 mg/kg. The highest dose of 60 mg/kg is approximately 418 times the clinical dose of 5 mg/day based on AUC exposure. Linagliptin did not increase the incidence of tumors in mice in a 2-year study at doses up to 80 mg/kg (males) and 25 mg/kg (females), or approximately 35 and 270 times the clinical dose based on AUC exposure. Higher doses of linagliptin in female mice (80 mg/kg) increased the incidence of lymphoma at approximately 215 times the clinical dose based on AUC exposure.

Linagliptin was not mutagenic or clastogenic with or without metabolic activation in the Ames bacterial mutagenicity assay, a chromosomal aberration test in human lymphocytes, and an in vivo micronucleus assay.

In fertility studies in rats, linagliptin had no adverse effects on early embryonic development, mating, fertility, or bearing live young up to the highest dose of 240 mg/kg (approximately 943 times the clinical dose based on AUC exposure).

Metformin HCl

Long-term carcinogenicity studies have been performed in Sprague Dawley rats at doses of 150, 300, and 450 mg/kg/day in males and 150, 450, 900, and 1,200 mg/kg/day in females. These doses are approximately 2, 4, and 8 times in males, and 3, 7, 12, and 16 times in females of the maximum recommended human daily dose of 2,000 mg/kg/day based on body surface area comparisons. No evidence of carcinogenicity with metformin was found in either male or female rats. A carcinogenicity study was also performed in Tg.AC transgenic mice at doses of up to 2,000 mg/kg/day applied dermally. No evidence of carcinogenicity was observed in male or female mice.

Genotoxicity assessments in the Ames test, gene mutation test (mouse lymphoma cells), chromosomal aberrations test (human lymphocytes) and in vivo mouse micronucleus tests were negative.

Fertility of male or female rats was not affected by metformin when administered at doses up to 600 mg/kg/day, which is approximately 3 times the maximum recommended human daily dose based on body surface area comparisons.

14 CLINICAL STUDIES

14.1 Empagliflozin and Linagliptin Add-on Combination Therapy with Metformin for Glycemic Control

A total of 686 patients with type 2 diabetes mellitus participated in a double-blind, active-controlled trial to evaluate the efficacy of empagliflozin 10 mg or 25 mg in combination with linagliptin 5 mg, compared to the individual components.

Patients with type 2 diabetes mellitus inadequately controlled on at least 1,500 mg of metformin HCl per day entered a single-blind placebo run-in period for 2 weeks. At the end of the run-in period, patients who remained inadequately controlled and had an HbA1c between 7% and 10.5% were randomized 1:1:1:1:1 to one of 5 active-treatment arms of empagliflozin 10 mg or 25 mg, linagliptin 5 mg, or linagliptin 5 mg in combination with 10 mg or 25 mg empagliflozin as a fixed dose combination tablet.

At Week 24, empagliflozin 10 mg or 25 mg used in combination with linagliptin 5 mg provided statistically significant improvement in HbA1c (p-value <0.0001) and FPG (p-value <0.001) compared to the individual components in patients who had been inadequately controlled on metformin HCl (see Table 7, Figure 3). Treatment with empagliflozin 10 mg or 25 mg used in combination with linagliptin 5 mg also resulted in a statistically significant reduction in body weight compared to linagliptin 5 mg (p-value <0.0001). There was no statistically significant difference compared to empagliflozin alone.

Table 7 Glycemic Parameters at 24 Weeks in a Trial Comparing Empagliflozin in Combination with Linagliptin to the Individual Components as Add-on Therapy in Patients Inadequately Controlled on Metformin HCl
 | Empagliflozin 10 mg/ Linagliptin 5 mg | Empagliflozin 25 mg/ Linagliptin 5 mg | Empagliflozin 10 mg | Empagliflozin 25 mg | Linagliptin 5 mg
HbA1c (%)
Number of patients | n=135 | n=133 | n=137 | n=139 | n=128
Baseline (mean) | 8.0 | 7.9 | 8.0 | 8.0 | 8.0
Change from baseline (adjusted mean) | -1.1 | -1.2 | -0.7 | -0.6 | -0.7
Comparison vs empagliflozin 25 mg or 10 mg (adjusted mean) (95% CI)a | -0.4 (-0.6, -0.2)d | -0.6 (-0.7, -0.4)d | -- | -- | --
Comparison vs linagliptin 5 mg (adjusted mean) (95% CI)a | -0.4 (-0.6, -0.2)d | -0.5 (-0.7, -0.3)d | -- | -- | --
Patients [n (%)] achieving HbA1c <7%b | 74 (58) | 76 (62) | 35 (28) | 43 (33) | 43 (36)
FPG (mg/dL)
Number of patients | n=133 | n=131 | n=136 | n=137 | n=125
Baseline (mean) | 157 | 155 | 162 | 160 | 156
Change from baseline (adjusted mean) | -33 | -36 | -21 | -21 | -13
Comparison vs empagliflozin 25 mg or 10 mg (adjusted mean) (95% CI)a | -12 (-18, -5)d | -15 (-22, -9)d | -- | -- | --
Comparison vs linagliptin 5 mg (adjusted mean) (95% CI)a | -20 (-27, -13)d | -23 (-29, -16)d | -- | -- | --
Body Weight
Number of patients | n=135 | n=134 | n=137 | n=140 | n=128
Baseline (mean) in kg | 87 | 85 | 86 | 88 | 85
% change from baseline (adjusted mean) | -3.1 | -3.4 | -3.0 | -3.5 | -0.7
Comparison vs empagliflozin 25 mg or 10 mg (adjusted mean) (95% CI)c | 0.0 (-0.9, 0.8) | 0.1 (-0.8, 0.9) | -- | -- | --
Comparison vs linagliptin 5 mg (adjusted mean) (95% CI)c | -2.4 (-3.3, -1.5)d | -2.7 (-3.6, -1.8)d | -- | -- | --
aFull analysis population (observed case) using MMRM. MMRM model included treatment, renal function, region, visit, visit by treatment interaction, and baseline HbA1c.
bPatients with HbA1c above 7% at baseline: empagliflozin 25 mg/linagliptin 5 mg, n=123; empagliflozin 10 mg/linagliptin 5 mg, n=128; empagliflozin 25 mg, n=132; empagliflozin 10 mg, n=125; linagliptin 5 mg, n=119. Non-completers were considered failures (NCF).
cFull analysis population using last observation carried forward. ANCOVA model included treatment, renal function, region, baseline weight, and baseline HbA1c.
dp<0.001 for FPG; p<0.0001 for HbA1c and body weight

Figure 3 Adjusted Mean HbA1c Change at Each Time Point (Completers) and at Week 24 (mITT population)

14.2 Empagliflozin Cardiovascular Outcomes in Patients with Type 2 Diabetes Mellitus and Atherosclerotic Cardiovascular Disease

EMPA-REG OUTCOME was a multicenter, multinational, randomized, double-blind parallel group trial that compared the risk of experiencing a major adverse cardiovascular event (MACE) between empagliflozin and placebo when these were added to and used concomitantly with standard of care treatments for diabetes mellitus and atherosclerotic CV disease. Concomitant antidiabetic medications were kept stable for the first 12 weeks of the trial. Thereafter, antidiabetic and atherosclerotic therapies could be adjusted, at the discretion of investigators, to ensure participants were treated according to the standard care for these diseases.

A total of 7,020 patients were treated (empagliflozin 10 mg = 2,345; empagliflozin 25 mg = 2,342; placebo = 2,333) and followed for a median of 3.1 years. Approximately 72% of the trial population was White, 22% was Asian, and 5% was Black or African American. The mean age was 63 years and approximately 72% were male.

All patients in the trial had inadequately controlled type 2 diabetes mellitus at baseline (HbA1c greater than or equal to 7%). The mean HbA1c at baseline was 8.1% and 57% of participants had diabetes mellitus for more than 10 years. Approximately 31%, 22% and 20% reported a past history of neuropathy, retinopathy and nephropathy to investigators, respectively and the mean eGFR was 74 mL/min/1.73 m^2. At baseline, patients were treated with one (~30%) or more (~70%) antidiabetic medications including metformin HCl (74%), insulin (48%), sulfonylurea (43%) and dipeptidyl peptidase-4 inhibitor (11%).

All patients had established atherosclerotic CV disease at baseline including one (82%) or more (18%) of the following: a documented history of coronary artery disease (76%), stroke (23%) or peripheral artery disease (21%). At baseline, the mean systolic blood pressure was 136 mmHg, the mean diastolic blood pressure was 76 mmHg, the mean LDL was 86 mg/dL, the mean HDL was 44 mg/dL, and the mean urinary albumin to creatinine ratio (UACR) was 175 mg/g. At baseline, approximately 81% of patients were treated with renin angiotensin system inhibitors, 65% with beta-blockers, 43% with diuretics, 77% with statins, and 86% with antiplatelet agents (mostly aspirin).

The primary endpoint in EMPA-REG OUTCOME was the time to first occurrence of a Major Adverse Cardiac Event (MACE). A major adverse cardiac event was defined as occurrence of either a CV death or a non-fatal myocardial infarction (MI) or a non-fatal stroke. The statistical analysis plan had pre-specified that the 10 and 25 mg doses would be combined. A Cox proportional hazards model was used to test for non-inferiority against the pre-specified risk margin of 1.3 for the hazard ratio of MACE and superiority on MACE if non-inferiority was demonstrated. Type-1 error was controlled across multiples tests using a hierarchical testing strategy.

Empagliflozin significantly reduced the risk of first occurrence of primary composite endpoint of CV death, non-fatal myocardial infarction, or non-fatal stroke (HR: 0.86; 95% CI: 0.74, 0.99). The treatment effect was due to a significant reduction in the risk of CV death in subjects randomized to empagliflozin (HR: 0.62; 95% CI: 0.49, 0.77), with no change in the risk of non-fatal myocardial infarction or non-fatal stroke (see Table 8 and Figures 4 and 5). Results for the 10 mg and 25 mg empagliflozin dosages were consistent with results for the combined dose groups.

Table 8 Treatment Effect for the Primary Composite Endpoint and its Componentsa
 | Placebo N=2,333 | Empagliflozin N=4,687 | Hazard ratio vs placebo (95% CI)
Composite of CV death, non-fatal myocardial infarction, non-fatal stroke (time to first occurrence)b | 282 (12.1%) | 490 (10.5%) | 0.86 (0.74, 0.99)
Non-fatal myocardial infarctionc | 121 (5.2%) | 213 (4.5%) | 0.87 (0.70, 1.09)
Non-fatal strokec | 60 (2.6%) | 150 (3.2%) | 1.24 (0.92, 1.67)
CV deathc | 137 (5.9%) | 172 (3.7%) | 0.62 (0.49, 0.77)
aTreated set (patients who had received at least one dose of trial drug)
bp−value for superiority (2−sided) 0.04
cTotal number of events

Figure 4 Estimated Cumulative Incidence of First MACE

Figure 5 Estimated Cumulative Incidence of CV Death

The efficacy of empagliflozin on CV death was generally consistent across major demographic and disease subgroups.

Vital status was obtained for 99.2% of subjects in the trial. A total of 463 deaths were recorded during the EMPA-REG OUTCOME trial. Most of these deaths were categorized as CV deaths. The non-CV deaths were only a small proportion of deaths and were balanced between the treatment groups (2.1% in patients treated with empagliflozin, and 2.4% of patients treated with placebo).

14.3 Linagliptin Cardiovascular Safety Trials in Patients with Type 2 Diabetes Mellitus

CARMELINA

The CV risk of linagliptin was evaluated in CARMELINA (NCT01897532), a multinational, multi-center, placebo-controlled, double-blind, parallel group trial comparing linagliptin (N=3,494) to placebo (N=3,485) in adult patients with type 2 diabetes mellitus and a history of established macrovascular and/or renal disease. The trial compared the risk of major adverse cardiovascular events (MACE) between linagliptin and placebo when these were added to standard of care treatments for diabetes mellitus and other CV risk factors. The trial was event driven, the median duration of follow-up was 2.2 years and vital status was obtained for 99.7% of patients.

Patients were eligible to enter the trial if they were adults with type 2 diabetes mellitus, with HbA1c of 6.5% to 10%, and had either albuminuria and previous macrovascular disease (39% of enrolled population), or evidence of impaired renal function by eGFR and Urinary Albumin Creatinine Ratio (UACR) criteria (42% of enrolled population), or both (18% of enrolled population).

At baseline the mean age was 66 years, and the population was 63% male, 80% White, 9% Asian, 6% Black or African American and 36% were of Hispanic or Latino ethnicity. Mean HbA1c was 8.0% and mean duration of type 2 diabetes mellitus was 15 years. The trial population included 17% patients ≥75 years of age and 62% patients with renal impairment defined as eGFR <60 mL/min/1.73 m^2. The mean eGFR was 55 mL/min/1.73 m^2 and 27% of patients had mild renal impairment (eGFR 60 to 90 mL/min/1.73 m^2), 47% of patients had moderate renal impairment (eGFR 30 to <60 mL/min/1.73 m^2) and 15% of patients had severe renal impairment (eGFR <30 mL/min/1.73 m^2). Patients were taking at least one antidiabetic drug (97%), and the most common were insulin and analogues (57%), metformin HCl (54%) and sulfonylurea (32%). Patients were also taking antihypertensives (96%), lipid lowering drugs (76%) with 72% on statin, and aspirin (62%).

The primary endpoint, MACE, was the time to first occurrence of one of three composite outcomes which included CV death, non-fatal myocardial infarction or non-fatal stroke. The trial was designed as a non-inferiority trial with a pre-specified risk margin of 1.3 for the hazard ratio of MACE. A total of 434 patients on linagliptin and 420 patients on placebo experienced MACE. The incidence rate of MACE in both treatment arms: 56.3 MACE per 1,000 patient-years on placebo vs. 57.7 MACE per 1,000 patient-years on linagliptin. The estimated hazard ratio for MACE associated with linagliptin relative to placebo was 1.02 with a 95% confidence interval of (0.89, 1.17). The upper bound of this confidence interval, 1.17, excluded the risk margin of 1.3.

CAROLINA

The CV risk of linagliptin was evaluated in CAROLINA, a multi-center, multinational, randomized, double-blind parallel group trial comparing linagliptin (N=3,023) to glimepiride (N=3,010) in adult patients with type 2 diabetes mellitus and a history of established CV disease and/or multiple CV risk factors. The trial compared the risk of major adverse cardiovascular events (MACE) between linagliptin and glimepiride when these were added to standard of care treatments for diabetes mellitus and other CV risk factors. The trial was event driven, the median duration of follow-up was 6.23 years and vital status was obtained for 99.3% of patients.

Patients were eligible to enter the trial if they were adults with type 2 diabetes mellitus with insufficient glycemic control (defined as HbA1c of 6.5% to 8.5% or 6.5% to 7.5% depending on treatment-naïve, on monotherapy or on combination therapy), and were defined to be at high CV risk with previous vascular disease, evidence of vascular related end-organ damage, age ≥70 years, and/or two CV risk factors (duration of diabetes mellitus >10 years, systolic blood pressure >140 mmHg, current smoker, LDL cholesterol ≥135 mg/dL).

At baseline the mean age was 64 years and the population was 60% male, 73% White, 18% Asian, 5% Black or African American, and 17% were of Hispanic or Latino ethnicity. The mean HbA1c was 7.15% and mean duration of type 2 diabetes mellitus was 7.6 years. The trial population included 34% patients ≥70 years of age and 19% patients with renal impairment defined as eGFR <60 mL/min/1.73 m^2. The mean eGFR was 77 mL/min/1.73 m^2. Patients were taking at least one antidiabetic drug (91%) and the most common were metformin HCl (83%) and sulfonylurea (28%). Patients were also taking antihypertensives (89%), lipid lowering drugs (70%) with 65% on statin, and aspirin (47%).

The primary endpoint, MACE, was the time to first occurrence of one of three composite outcomes which included CV death, non-fatal myocardial infarction or non-fatal stroke. The trial was designed as a non-inferiority trial with a pre-specified risk margin of 1.3 for the hazard ratio of MACE. A total of 356 patients on linagliptin and 362 patients on glimepiride experienced MACE. The incidence rate of MACE in both treatment arms: 20.7 MACE per 1,000 patient-years on linagliptin vs. 21.2 MACE per 1,000 patient-years on glimepiride. The estimated hazard ratio for MACE associated with linagliptin relative to glimepiride was 0.98 with a 95% confidence interval of (0.84, 1.14). The upper bound of this confidence interval, 1.14, excluded the risk margin of 1.3.

16 HOW SUPPLIED/STORAGE AND HANDLING

TRIJARDY XR tablets are available as follows:

Tablet Strength | Color/Shape | Tablet Markings | Package Size | NDC Number
5 mg Empagliflozin 2.5 mg Linagliptin 1,000 mg Metformin HCl Extended-Release | grey, oval-shaped, film-coated tablet | Printed on one side in white ink with the Boehringer Ingelheim company symbol and "395" on the top line and "5/2.5" on the bottom line. | Bottles of 60 Bottles of 180 | 0597-0395-82 0597-0395-23
10 mg Empagliflozin 5 mg Linagliptin 1,000 mg Metformin HCl Extended-Release | tan, oval-shaped, film-coated tablet | Printed on one side in white ink with the Boehringer Ingelheim company symbol and "380" on the top line and "10/5" on the bottom line. | Bottles of 30 Bottles of 90 | 0597-0380-13 0597-0380-68
12.5 mg Empagliflozin 2.5 mg Linagliptin 1,000 mg Metformin HCl Extended-Release | red, oval-shaped, film-coated tablet | Printed on one side in white ink with the Boehringer Ingelheim company symbol and "385" on the top line and "12.5/2.5" on the bottom line. | Bottles of 60 Bottles of 180 | 0597-0385-77 0597-0385-86
25 mg Empagliflozin 5 mg Linagliptin 1,000 mg Metformin HCl Extended-Release | brown, oval-shaped, film-coated tablet | Printed on one side in white ink with the Boehringer Ingelheim company symbol and "390" on the top line and "25/5" on the bottom line. | Bottles of 30 Bottles of 90 | 0597-0390-71 0597-0390-13

Storage

Store at 20°C to 25°C (68°F to 77°F); excursions permitted to 15°C to 30°C (59°F to 86°F) [see USP Controlled Room Temperature]. Protect from exposure to high humidity.

17 PATIENT COUNSELING INFORMATION

Advise the patient to read the FDA-approved patient labeling (Medication Guide).

Lactic Acidosis

Inform patients of the risks of lactic acidosis due to metformin, its symptoms, and conditions that predispose to its development. Advise patients to discontinue TRIJARDY XR immediately and to notify their healthcare provider promptly if unexplained hyperventilation, malaise, myalgia, unusual somnolence, or other nonspecific symptoms occur. Counsel patients against excessive alcohol intake and inform patients about importance of regular testing of renal function while receiving TRIJARDY XR. Instruct patients to inform their healthcare provider that they are taking TRIJARDY XR prior to any surgical or radiological procedure, as temporary discontinuation may be required until renal function has been confirmed to be normal [see Warnings and Precautions (5.1)].

Diabetic Ketoacidosis in Patients with Type 1 Diabetes Mellitus and Other Ketoacidosis

Inform patients that TRIJARDY XR can cause potentially fatal ketoacidosis and that type 2 diabetes mellitus and pancreatic disorders (e.g., history of pancreatitis or pancreatic surgery) are risk factors.

Educate all patients on precipitating factors (such as insulin dose reduction or missed insulin doses, infection, reduced caloric intake, ketogenic diet, surgery, dehydration, and alcohol abuse) and symptoms of ketoacidosis (including nausea, vomiting, abdominal pain, tiredness, and labored breathing). Inform patients that blood glucose may be normal even in the presence of ketoacidosis.

Advise patients that they may be asked to monitor ketones. If symptoms of ketoacidosis occur, instruct patients to discontinue TRIJARDY XR and seek medical attention immediately [see Warnings and Precautions (5.2)].

Pancreatitis

Inform patients that acute pancreatitis has been reported during use of linagliptin. Inform patients that persistent severe abdominal pain, sometimes radiating to the back, which may or may not be accompanied by vomiting, is the hallmark symptom of acute pancreatitis. Instruct patients to discontinue TRIJARDY XR promptly and contact their healthcare provider if persistent severe abdominal pain occurs [see Warnings and Precautions (5.3)].

Volume Depletion

Inform patients that symptomatic hypotension may occur with TRIJARDY XR and advise them to contact their healthcare provider if they experience such symptoms [see Warnings and Precautions (5.4)]. Inform patients that dehydration may increase the risk for hypotension, and to maintain adequate fluid intake.

Genitourinary Infections, including Urosepsis, Pyelonephritis, Necrotizing Fasciitis of the Perineum (Fournier's Gangrene), and Genital Mycotic Infections

Counsel patients that genitourinary infections may occur when taking empagliflozin, a component of TRIJARDY XR, and may become serious. Educate them on the symptoms and advise them to seek medical advice if symptoms occur. Specifically, advise patients to promptly seek medical attention if they develop pain or tenderness, redness, or swelling of the genitals or the area from the genitals back to the rectum, along with a fever above 100.4°F or malaise [see Warnings and Precautions (5.5)].

Hypoglycemia with Concomitant Use with Insulin and Insulin Secretagogues

Inform patients that the risk of hypoglycemia is increased when TRIJARDY XR is used in combination with an insulin secretagogue (e.g., sulfonylurea) or insulin [see Warnings and Precautions (5.6)].

Lower Limb Amputation

Counsel patients about the importance of routine preventative foot care. Instruct patients to monitor for new pain or tenderness, sores or ulcers, or infections involving the leg or foot and to seek medical advice immediately if such signs or symptoms develop [see Warnings and Precautions (5.7)].

Hypersensitivity Reactions

Inform patients that serious allergic reactions, such as anaphylaxis, angioedema, and exfoliative skin conditions, have been reported during postmarketing use of linagliptin or empagliflozin, components of TRIJARDY XR. If symptoms of allergic reactions (such as rash, skin flaking or peeling, urticaria, swelling of the skin, or swelling of the face, lips, tongue, and throat that may cause difficulty in breathing or swallowing) occur, patients must stop taking TRIJARDY XR and seek medical advice promptly [see Warnings and Precautions (5.8)].

Vitamin B12 Deficiency

Inform patients about the importance of regular hematological parameters while receiving TRIJARDY XR [see Warnings and Precautions (5.9)].

Severe and Disabling Arthralgia

Inform patients that severe and disabling joint pain may occur with this class of drugs. The time to onset of symptoms can range from one day to years. Instruct patients to seek medical advice if severe joint pain occurs [see Warnings and Precautions (5.10)].

Bullous Pemphigoid

Inform patients that bullous pemphigoid has been reported during use of linagliptin. Instruct patients to seek medical advice if blisters or erosions occur [see Warnings and Precautions (5.11)].

Heart Failure

Inform patients of the signs and symptoms of heart failure. Before initiating TRIJARDY XR, patients should be asked about a history of heart failure or other risk factors for heart failure including moderate to severe renal impairment. Instruct patients to contact their healthcare provider as soon as possible if they experience symptoms of heart failure, including increasing shortness of breath, rapid increase in weight or swelling of the feet [see Warnings and Precautions (5.12)].

Laboratory Tests

Inform patients that elevated glucose in urinalysis is expected when taking TRIJARDY XR [see Drug Interactions (7)].

Pregnancy

Advise pregnant patients, and patients of reproductive potential, of the potential risk to a fetus with treatment with TRIJARDY XR [see Use in Specific Populations (8.1)]. Instruct patients to report pregnancies to their healthcare provider as soon as possible.

Lactation

Advise patients that breastfeeding is not recommended during treatment with TRIJARDY XR [see Use in Specific Populations (8.2)].

Patients of Reproductive Potential

Inform patients that treatment with metformin HCl may result in ovulation in some premenopausal anovulatory patients, which may lead to unintended pregnancy [see Use in Specific Populations (8.3)].

Administration Instructions

Inform patients that the tablets must be swallowed whole and never split, crushed, dissolved, or chewed and that incompletely dissolved TRIJARDY XR tablets may be eliminated in the feces.

Missed Dose

Instruct patients to take TRIJARDY XR only as prescribed. If a dose is missed, it should be taken as soon as the patient remembers. Advise patients not to double their next dose [see Dosage and Administration (2.6)].

Distributed by:
Boehringer Ingelheim Pharmaceuticals, Inc.
Ridgefield, CT 06877 USA

Licensed from:
Boehringer Ingelheim International GmbH, Ingelheim, Germany.

TRIJARDY is a registered trademark of and used under license from Boehringer Ingelheim International GmbH.

Boehringer Ingelheim Pharmaceuticals, Inc. either owns or uses the Jardiance®, Tradjenta®, EMPA-REG OUTCOME®, CARMELINA®, and CAROLINA® trademarks under license.

The other brands listed are trademarks of their respective owners and are not trademarks of Boehringer Ingelheim Pharmaceuticals, Inc.

Copyright © 2026 Boehringer Ingelheim International GmbH
ALL RIGHTS RESERVED

COL9014GA062026

SPL9015I

MEDICATION GUIDE
TRIJARDY® XR (try-JAR-dee XR)
(empagliflozin, linagliptin, and metformin hydrochloride extended-release tablets)
for oral use

What is the most important information I should know about TRIJARDY XR?
TRIJARDY XR can cause serious side effects, including:

1. Lactic Acidosis. Metformin hydrochloride (HCl), one of the medicines in TRIJARDY XR, can cause a rare but serious condition called lactic acidosis (a build-up of lactic acid in the blood) that can cause death. Lactic acidosis is a medical emergency and must be treated in a hospital.
  Stop taking TRIJARDY XR and call your healthcare provider right away or go to the nearest hospital emergency room if you get any of the following symptoms of lactic acidosis:

- feel very weak and tired
- have unusual (not normal) muscle pain
- have trouble breathing
- have unexplained stomach or intestinal problems with nausea and vomiting, or diarrhea

- have unusual sleepiness or sleep longer than usual
- feel cold, especially in your arms and legs
- feel dizzy or lightheaded
- have a slow or irregular heartbeat

You have a higher chance of getting lactic acidosis with TRIJARDY XR if you:

- have moderate to severe kidney problems.
- have liver problems.
- drink a lot of alcohol (very often or short-term "binge" drinking).
- get dehydrated (lose a large amount of body fluids). This can happen if you are sick with a fever, vomiting, or diarrhea. Dehydration can also happen when you sweat a lot with activity or exercise and do not drink enough fluids.
- have certain x-ray tests with injectable dyes or contrast agents.
- have surgery or other procedure for which you need to restrict the amount of food and liquid you eat and drink.
- have congestive heart failure.
- have a heart attack, severe infection, or stroke.
- are 65 years of age or older.

Tell your healthcare provider if you have any of the problems in the list above. Tell your healthcare provider that you are taking TRIJARDY XR before you have surgery or x-ray tests. Your healthcare provider may need to stop your TRIJARDY XR for a while if you have surgery or certain x-ray tests. TRIJARDY XR can have other serious side effects. See "What are the possible side effects of TRIJARDY XR?"

2. Diabetic ketoacidosis (increased ketones in your blood or urine) in people with type 1 and other ketoacidosis. TRIJARDY XR can cause ketoacidosis that can be life-threatening and may lead to death. Ketoacidosis is a serious condition which needs to be treated in a hospital. People with type 1 diabetes have a high risk of getting ketoacidosis. People with type 2 diabetes or pancreas problems also have an increased risk of getting ketoacidosis. Ketoacidosis can also happen in people who: are sick, cannot eat or drink as usual, skip meals, are on a diet high in fat and low in carbohydrates (ketogenic diet), take less than the usual amount of insulin or miss insulin doses, drink too much alcohol, have a loss of too much fluid from the body (volume depletion), or who have surgery. Ketoacidosis can happen even if your blood sugar is less than 250 mg/dL. Your healthcare provider may ask you to periodically check ketones in your urine or blood.
  Stop taking TRIJARDY XR and call your healthcare provider or get medical help right away if you get any of the following. If possible, check for ketones in your urine or blood, even if your blood sugar is less than 250 mg/dL:

- nausea
- vomiting
- stomach-area (abdominal) pain

- tiredness
- trouble breathing
- ketones in your urine or blood

3. Inflammation of the pancreas (pancreatitis) which may be severe and lead to death. Certain medical problems make you more likely to get pancreatitis.
  Before you start taking TRIJARDY XR, tell your healthcare provider if you have ever had:

- inflammation of your pancreas (pancreatitis)
- a history of alcoholism

- stones in your gallbladder (gallstones)
- high blood triglyceride levels

Stop taking TRIJARDY XR and call your healthcare provider right away if you have pain in your stomach area (abdomen) that is severe and will not go away. The pain may be felt going from your abdomen to your back. The pain may happen with or without vomiting. These may be symptoms of pancreatitis.

4. Dehydration. TRIJARDY XR can cause some people to become dehydrated (the loss of body water and salt). Dehydration may cause you to feel dizzy, faint, light-headed, or weak, especially when you stand up (orthostatic hypotension). There have been reports of sudden worsening of kidney function in people who are taking TRIJARDY XR. You may be at higher risk of dehydration if you:
  - take medicines to lower your blood pressure, including diuretics (water pills)
  - are on a low sodium (salt) diet
  - have kidney problems
  - are 65 years of age or older
  Talk to your healthcare provider about what you can do to prevent dehydration including how much fluid you should drink on a daily basis. Call your healthcare provider right away if you reduce the amount of food or liquid you drink, for example if you are sick or you cannot eat, or start to lose liquids from your body, for example from vomiting, diarrhea or being in the sun too long.

What is TRIJARDY XR?
TRIJARDY XR is a prescription medicine that contains 3 diabetes medicines, empagliflozin (JARDIANCE), linagliptin (TRADJENTA), and metformin HCl. TRIJARDY XR can be used:

  - along with diet and exercise to lower blood sugar (glucose) in adults with type 2 diabetes,
  - in adults with type 2 diabetes who have known cardiovascular disease when empagliflozin (JARDIANCE), one of the medicines in TRIJARDY XR, is needed to reduce the risk of cardiovascular death.

- TRIJARDY XR is not for use to lower blood sugar (glucose) in people with type 1 diabetes. It may increase their risk of diabetic ketoacidosis (increased ketones in blood or urine).
- If you have had pancreatitis in the past, it is not known if you have a higher chance of getting pancreatitis while you take TRIJARDY XR.
- It is not known if TRIJARDY XR is safe and effective in children.

Who should not take TRIJARDY XR?
Do not take TRIJARDY XR if you:

- have severe kidney problems.
- have a condition called metabolic acidosis or diabetic ketoacidosis (increased ketones in the blood or urine).
- are allergic to empagliflozin (JARDIANCE), linagliptin (TRADJENTA), metformin HCl, or any of the ingredients in TRIJARDY XR. See the end of this Medication Guide for a complete list of ingredients in TRIJARDY XR.
  Symptoms of a serious allergic reaction to TRIJARDY XR may include:
  - skin rash, itching, flaking or peeling
  - raised red patches on your skin (hives)
  - swelling of your face, lips, tongue and throat that may cause difficulty in breathing or swallowing
  - difficulty with swallowing or breathing
  If you have any of these symptoms, stop taking TRIJARDY XR and call your healthcare provider right away or go to the nearest hospital emergency room.

What should I tell my healthcare provider before taking TRIJARDY XR?
Before taking TRIJARDY XR, tell your healthcare provider about all of your medical conditions, including if you:

- have type 1 diabetes or have had diabetic ketoacidosis.
- have a decrease in your insulin dose.
- have a serious infection.
- have a history of infection of the vagina or penis.
- have a history of amputation.
- have kidney problems.
- have liver problems.
- have heart problems, including congestive heart failure.
- are 65 years of age or older.
- have a history of urinary tract infections or problems with urination.
- are on a low sodium (salt) diet. Your healthcare provider may change your diet or your dose.
- are going to have surgery. Your healthcare provider may stop your TRIJARDY XR before you have surgery. Talk to your healthcare provider if you are having surgery about when to stop taking TRIJARDY XR and when to start it again.
- are eating less, or there is a change in your diet.
- are dehydrated.
- have or have had problems with your pancreas, including pancreatitis or surgery on your pancreas.
- drink alcohol very often or drink a lot of alcohol in the short term ("binge" drinking).
- have ever had an allergic reaction to TRIJARDY XR.
- are going to get an injection of dye or contrast agents for an x-ray procedure. TRIJARDY XR may need to be stopped for a short time. Talk to your healthcare provider about when you should stop TRIJARDY XR and when you should start TRIJARDY XR again. See "What is the most important information I should know about TRIJARDY XR?"
- have low levels of vitamin B12 in your blood.
- are pregnant or plan to become pregnant. TRIJARDY XR may harm your unborn baby. If you become pregnant while taking TRIJARDY XR, tell your healthcare provider as soon as possible. Talk with your healthcare provider about the best way to control your blood sugar while you are pregnant.
- are breastfeeding or plan to breastfeed. TRIJARDY XR may pass into your breast milk and may harm your baby. Talk with your healthcare provider about the best way to feed your baby if you are taking TRIJARDY XR. Do not breastfeed while taking TRIJARDY XR.
- are a person who has not gone through menopause (premenopausal) who does not have periods regularly or at all. TRIJARDY XR can cause the release of an egg from an ovary in a person (ovulation). This can increase your chance of getting pregnant. Tell your healthcare provider right away if you become pregnant while taking TRIJARDY XR.

Tell your healthcare provider about all the medicines you take, including prescription and over-the-counter medicines, vitamins, and herbal supplements.
TRIJARDY XR may affect the way other medicines work, and other medicines may affect how TRIJARDY XR works.
Know the medicines you take. Keep a list of them to show your healthcare provider and pharmacist when you get a new medicine.

How should I take TRIJARDY XR?

- Take TRIJARDY XR exactly as your healthcare provider tells you to take it.
- Take TRIJARDY XR by mouth 1 time each day with a meal in the morning. Taking TRIJARDY XR with a meal may lower your chance of having an upset stomach.
- Swallow TRIJARDY XR tablets whole. Do not break, cut, crush, dissolve, or chew TRIJARDY XR. If you cannot swallow TRIJARDY XR tablets whole, tell your healthcare provider.
- You may see something that looks like the TRIJARDY XR tablet in your stool (bowel movement). This is not harmful and should not affect the way TRIJARDY XR works to control your diabetes.
- Your healthcare provider will tell you how much TRIJARDY XR to take and when to take it. Your healthcare provider may change your dose if needed.
- Your healthcare provider may tell you to take TRIJARDY XR along with other diabetes medicines. Low blood sugar can happen more often when TRIJARDY XR is taken with certain other diabetes medicines. See "What are the possible side effects of TRIJARDY XR?"
- If you miss a dose, take it as soon as you remember. If it is almost time for your next dose, skip the missed dose and take the medicine at the next regularly scheduled time. Do not take two doses of TRIJARDY XR at the same time. Talk with your healthcare provider if you have questions about a missed dose.
- If you take too much TRIJARDY XR, call your healthcare provider or Poison Help line at 1-800-222-1222, or go to the nearest hospital emergency room right away.
- When taking TRIJARDY XR, you may have sugar in your urine, which will show up on a urine test.
- When your body is under some types of stress, such as fever, trauma (such as a car accident), infection, or surgery, the amount of diabetes medicine you need may change. Tell your healthcare provider right away if you have any of these conditions and follow your healthcare provider's instructions.
- Your healthcare provider may do certain blood tests before you start TRIJARDY XR and during treatment as needed.

What should I avoid while taking TRIJARDY XR?
Avoid drinking alcohol very often or drinking a lot of alcohol in a short period of time ("binge" drinking). It can increase your chances of getting serious side effects.

What are the possible side effects of TRIJARDY XR?
TRIJARDY XR may cause serious side effects, including:

- See "What is the most important information I should know about TRIJARDY XR?"
- Genital and urinary tract infections. Empagliflozin, one of the medicines in TRIJARDY XR, can cause serious infections in your genital area or urinary tract that could require hospitalization. A rare but serious bacterial infection called necrotizing fasciitis can cause damage to the tissue under the skin in the area between and around the anus and genitals (perineum). This infection may require hospitalization, multiple surgeries, and could lead to death. Seek medical attention immediately if you have a fever or you are feeling very weak, tired or uncomfortable (malaise), and you develop any of the following symptoms in the area between and around your anus and genitals:

- pain or tenderness

- swelling

- redness of skin (erythema)

Also tell your healthcare provider if you have any of these signs or symptoms of urinary tract infections or yeast infections:

- Urinary tract infection:

- burning feeling when you urinate
- need to urinate often or right away
- pain in the lower part of your stomach (pelvis)
- blood in your urine

You may also have a fever, back pain, nausea, or vomiting.

- Vaginal yeast infection:

- vaginal odor
- white or yellowish vaginal discharge (may be lumpy or look like cottage cheese)
- vaginal itching

- Yeast infection of the skin around the penis (balanitis or balanoposthitis): If you are uncircumcised, swelling may make it difficult to pull back the skin around the tip of your penis. Other symptoms include:

- redness, itching, or swelling of the penis
- bad smelling discharge from the penis

- rash on the penis
- pain in the skin around the penis

Talk to your healthcare provider about what to do if you get symptoms of a yeast infection. They may suggest you use an over-the-counter antifungal medicine. Contact your healthcare provider right away if your symptoms do not improve after using an over-the-counter antifungal medicine.

- Low blood sugar (hypoglycemia). If you take TRIJARDY XR with another medicine that can cause low blood sugar, such as a sulfonylurea or insulin, your risk of getting low blood sugar is higher. The dose of your sulfonylurea medicine or insulin may need to be lowered while you take TRIJARDY XR. Signs and symptoms of low blood sugar may include:

- headache
- drowsiness
- weakness

- irritability
- hunger
- fast heartbeat

- confusion
- shaking or feeling jittery

- dizziness
- sweating

- Amputations. SGLT2 inhibitors may increase your risk of lower limb amputations.
  You may be at a higher risk of lower limb amputation if you:
  - have a history of amputation
  - have had blocked or narrowed blood vessels, usually in your leg
  - have had diabetic foot infection, ulcers or sores
  Call your healthcare provider right away if you have new pain or tenderness, any sores, ulcers, or infections in your leg or foot. Talk to your healthcare provider about proper foot care.
- Serious allergic reactions. If you have any symptoms of a serious allergic reaction, stop taking TRIJARDY XR and call your healthcare provider right away or go to the nearest hospital emergency room. See "Who should not take TRIJARDY XR?".
- Low vitamin B12 (vitamin B12 deficiency). Using metformin for long periods of time may cause a decrease in the amount of vitamin B12 in your blood, especially if you have had low vitamin B12 blood levels before. Your healthcare provider may do blood tests to check your vitamin B12 levels.
- Joint pain. Some people who take linagliptin, one of the medicines in TRIJARDY XR, may develop joint pain that can be severe. Call your healthcare provider if you have severe joint pain.
- Skin reaction. Some people who take medicines called DPP-4 inhibitors, one of the medicines in TRIJARDY XR, may develop a skin reaction called bullous pemphigoid that can require treatment in a hospital. Tell your healthcare provider right away if you develop blisters or the breakdown of the outer layer of your skin (erosion). Your healthcare provider may tell you to stop taking TRIJARDY XR.
- Heart failure. Heart failure means your heart does not pump blood well enough.
  Before you start taking TRIJARDY XR, tell your healthcare provider if you have ever had heart failure or have problems with your kidneys. Contact your healthcare provider right away if you have any of the following symptoms:
  - increasing shortness of breath or trouble breathing, especially when you lie down
  - swelling or fluid retention, especially in the feet, ankles or legs
  - an unusually fast increase in weight
  - unusual tiredness
  These may be symptoms of heart failure.

The most common side effects of TRIJARDY XR include:

- upper respiratory tract infection
- urinary tract infection
- stuffy or runny nose and sore throat
- diarrhea

- constipation
- headache
- inflammation of the stomach and intestine (gastroenteritis)

Tell your healthcare provider if you have any side effect that bothers you or that does not go away.
These are not all the possible side effects of TRIJARDY XR. For more information, ask your healthcare provider or pharmacist.
Call your doctor for medical advice about side effects. You may report side effects to FDA at 1-800-FDA-1088.

How should I store TRIJARDY XR?

- Store TRIJARDY XR at room temperature between 68°F to 77°F (20°C to 25°C).
- Keep TRIJARDY XR tablets dry.
- Keep TRIJARDY XR and all medicines out of the reach of children.

General information about the safe and effective use of TRIJARDY XR.
Medicines are sometimes prescribed for purposes other than those listed in a Medication Guide. Do not use TRIJARDY XR for a condition for which it was not prescribed. Do not give TRIJARDY XR to other people, even if they have the same symptoms that you have. It may harm them.
You can ask your pharmacist or healthcare provider for information about TRIJARDY XR that is written for health professionals.

What are the ingredients in TRIJARDY XR?
Active ingredients: empagliflozin, linagliptin, and metformin hydrochloride
Inactive ingredients: Tablet core contains: hypromellose, magnesium stearate, and polyethylene oxide. The Film Coatings and Printing Ink contain: ammonium hydroxide, arginine, carnauba wax, ferric oxide yellow and ferric oxide red (10 mg/5 mg/1,000 mg), ferrosoferric oxide and ferric oxide red (12.5 mg/2.5 mg/1,000 mg), ferrosoferric oxide and ferric oxide yellow (5 mg/2.5 mg/1,000 mg and 25 mg/5 mg/1,000 mg), hydroxypropyl cellulose, hypromellose, isopropyl alcohol, n-butyl alcohol, polyethylene glycol, propylene glycol, purified water, shellac glaze, talc, and titanium dioxide.

Distributed by: Boehringer Ingelheim Pharmaceuticals, Inc., Ridgefield, CT 06877 USA
Licensed from: Boehringer Ingelheim International GmbH, Ingelheim, Germany
TRIJARDY is a registered trademark of and used under license from Boehringer Ingelheim International GmbH. Boehringer Ingelheim Pharmaceuticals, Inc. either owns or uses the Jardiance®, Tradjenta®, EMPA-REG OUTCOME®, CARMELINA®, and CAROLINA® trademarks under license.
The other brands listed are trademarks of their respective owners and are not trademarks of Boehringer Ingelheim Pharmaceuticals, Inc.
Copyright © 2026 Boehringer Ingelheim International GmbH
ALL RIGHTS RESERVED
COL9014GA062026
For more information about TRIJARDY XR, including current prescribing information and Medication Guide, go to www.trijardyxr.com, scan the code, or call Boehringer Ingelheim Pharmaceuticals, Inc. at 1-800-542-6257.

This Medication Guide has been approved by the U.S. Food and Drug Administration.

Revised: January 2026

PRINCIPAL DISPLAY PANEL - 5 mg/2.5 mg/1,000 mg Tablet Bottle Label

NDC 0597-0395-82

Trijardy®XR
(empagliflozin, linagliptin, and metformin
hydrochloride extended-release tablets)

5 mg/2.5 mg/1,000 mg*

DISPENSE WITH ACCOMPANYING MEDICATION GUIDE

60 tablets
Rx only

Boehringer
Ingelheim

PRINCIPAL DISPLAY PANEL - 10 mg/5 mg/1,000 mg Tablet Bottle Label

NDC 0597-0380-13

Trijardy®XR
(empagliflozin, linagliptin,
and metformin hydrochloride
extended-release tablets)

10 mg/5 mg/1,000 mg*

DISPENSE WITH ACCOMPANYING
MEDICATION GUIDE

30 tablets
Rx only

Boehringer
Ingelheim

PRINCIPAL DISPLAY PANEL - 12.5 mg/2.5 mg/1,000 mg Tablet Bottle Label

NDC 0597-0385-77

Trijardy®XR
(empagliflozin, linagliptin, and metformin
hydrochloride extended-release tablets)

12.5 mg/2.5 mg/1,000 mg*

DISPENSE WITH ACCOMPANYING MEDICATION GUIDE

60 tablets
Rx only

Boehringer
Ingelheim

PRINCIPAL DISPLAY PANEL - 25 mg/5 mg/1,000 mg Tablet Bottle Label

NDC 0597-0390-71

Trijardy®XR
(empagliflozin, linagliptin,
and metformin hydrochloride
extended-release tablets)

25 mg/5 mg/1,000 mg*

DISPENSE WITH ACCOMPANYING
MEDICATION GUIDE

30 tablets
Rx only

Boehringer
Ingelheim